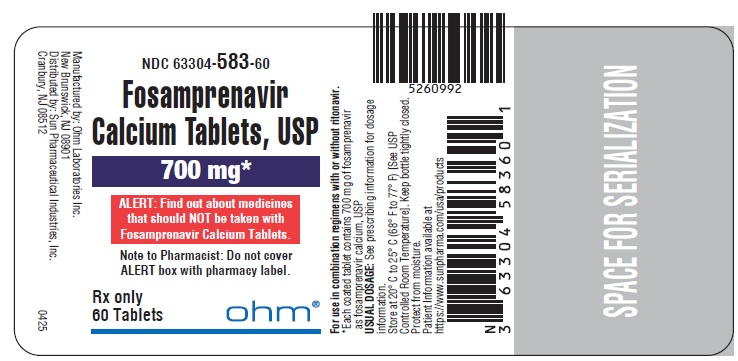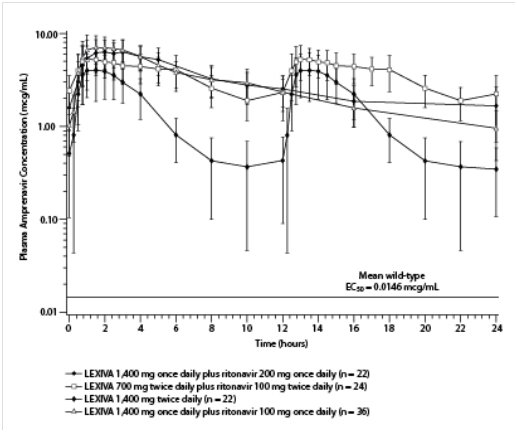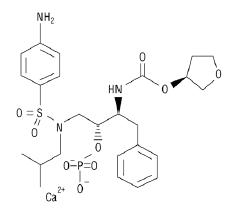 DRUG LABEL: Fosamprenavir Calcium
NDC: 63304-583 | Form: TABLET, COATED
Manufacturer: Sun Pharmaceutical Industries, Inc.
Category: prescription | Type: HUMAN PRESCRIPTION DRUG LABEL
Date: 20250425

ACTIVE INGREDIENTS: FOSAMPRENAVIR CALCIUM 700 mg/1 1
INACTIVE INGREDIENTS: CROSCARMELLOSE SODIUM; SILICON DIOXIDE; MICROCRYSTALLINE CELLULOSE; MAGNESIUM STEARATE; POVIDONE, UNSPECIFIED; HYPROMELLOSE, UNSPECIFIED; ETHYLCELLULOSE, UNSPECIFIED; TITANIUM DIOXIDE; TALC; FERRIC OXIDE RED; SHELLAC; FERROSOFERRIC OXIDE; PROPYLENE GLYCOL

HIGHLIGHTS OF PRESCRIBING INFORMATION

These highlights do not include all the information needed to use FOSAMPRENAVIR CALCIUM TABLETS safely and effectively. See full prescribing information for FOSAMPRENAVIR CALCIUM TABLETS.
FOSAMPRENAVIR CALCIUM tablets, for oral use
Initial U.S. Approval: 2003

1 INDICATIONS AND USAGE

Fosamprenavir calcium tablets are HIV protease inhibitor indicated in combination with other antiretroviral agents for the treatment of HIV-1 infection. (1)

2 DOSAGE AND ADMINISTRATION

- Therapy-Naive Adults: Fosamprenavir calcium tablets 1,400 mg twice daily; fosamprenavir calcium tablets 1,400 mg once daily plus ritonavir 200 mg once daily; fosamprenavir calcium tablets 1,400 mg once daily plus ritonavir 100 mg once daily; fosamprenavir calcium tablets 700 mg twice daily plus ritonavir 100 mg twice daily. (2.2)
- Protease Inhibitor-Experienced Adults: Fosamprenavir calcium tablets 700 mg twice daily plus ritonavir 100 mg twice daily. (2.2)
- Pregnant Patients: Fosamprenavir calcium tablets 700 mg twice daily plus ritonavir 100 mg twice daily should only be considered in women who are already on a stable twice-daily regimen of fosamprenavir calcium /ritonavir 700 mg/100 mg prior to pregnancy and who are virologically suppressed (HIV-1 RNA less than 50 copies per mL). (2.2)
- Pediatric Patients (aged at least 4 weeks to 18 years): Dosage should be calculated based on body weight (kg) and should not exceed adult dose. (2.3)
- Hepatic Impairment: Recommended adjustments for patients with mild, moderate, or severe hepatic impairment. (2.4)

Dosing Considerations

- Fosamprenavir calcium tablets may be taken with or without food. (2.1)
- Fosamprenavir Calcium Oral Suspension: Adults should take without food; pediatric patients should take with food. (2.1)

3 DOSAGE FORMS AND STRENGTHS

- 700 mg tablets (3)

4 CONTRAINDICATIONS

- Hypersensitivity to fosamprenavir calcium or amprenavir (e.g., Stevens-Johnson syndrome). (4)
- Drugs highly dependent on cytochrome P450 (CYP)3A4 for clearance and for which elevated plasma levels may result in serious and/or life-threatening events. (4)
- Review ritonavir contraindications when used in combination. (4)

5 WARNINGS AND PRECAUTIONS

- The concomitant use of fosamprenavir calcium with ritonavir and certain other drugs may result in known or potentially significant drug interactions. Consult the full prescribing information prior to and during treatment for potential drug interactions. (5.1, 7.3)
- Fosamprenavir calcium should be discontinued for severe skin reactions, including Stevens-Johnson syndrome. (5.2)
- Fosamprenavir calcium should be used with caution in patients with a known sulfonamide allergy. (5.3)
- Use of higher-than-approved doses may lead to transaminase elevations. Patients with hepatitis B or C are at increased risk of transaminase elevations. (5.4)
- Patients receiving fosamprenavir calcium may develop new onset or exacerbations of diabetes mellitus, hyperglycemia (5.5), immune reconstitution syndrome (5.6), increase of body fat (5.7), and elevated triglyceride and cholesterol concentrations (5.8). Monitor cholesterol and triglycerides prior to therapy and periodically thereafter.
- Acute hemolytic anemia has been reported with amprenavir. (5.9)
- Hemophilia: Spontaneous bleeding may occur, and additional factor VIII may be required. (5.10)
- Nephrolithiasis: Cases of nephrolithiasis have been reported with fosamprenavir. (5.11)

6 ADVERSE REACTIONS

- In adults the most common adverse reactions (incidence greater than or equal to 4%) are diarrhea, rash, nausea, vomiting, and headache. (6.1)
- Vomiting and neutropenia were more frequent in pediatrics than in adults. (6.1)

To report SUSPECTED ADVERSE REACTIONS, contact Sun Pharmaceutical Industries, Inc. at 1-800-406-7984 or FDA at 1-800-FDA-1088 or www.fda.gov/medwatch.

7 DRUG INTERACTIONS

- Coadministration of fosamprenavir calcium with drugs that induce CYP3A4 may decrease amprenavir (active metabolite) concentrations leading to potential loss of virologic activity. (7, 12.3)
- Coadministration with drugs that inhibit CYP3A4 may increase amprenavir concentrations. (7, 12.3)
- Coadministration of fosamprenavir calcium or fosamprenavir calcium and ritonavir may result in clinically significant interactions with drugs metabolized by CYP3A4. (7)
- Coadministration of fosamprenavir calcium and ritonavir may result in clinically significant interactions with drugs metabolized by CYP2D6. (7)

8 USE IN SPECIFIC POPULATIONS

Lactation: Breastfeeding is not recommended due to potential for HIV transmission. (8.2)

FULL PRESCRIBING INFORMATION

1 INDICATIONS AND USAGE

Fosamprenavir calcium tablets are indicated in combination with other antiretroviral agents for the treatment of human immunodeficiency virus (HIV-1) infection.

The following points should be considered when initiating therapy with fosamprenavir calcium tablets plus ritonavir in protease inhibitor-experienced patients:

- The protease inhibitor-experienced patient trial was not large enough to reach a definitive conclusion that fosamprenavir calcium tablets plus ritonavir and lopinavir plus ritonavir are clinically equivalent [see Clinical Studies (14.2)].
- Once-daily administration of fosamprenavir calcium tablets plus ritonavir is not recommended for adult protease inhibitor-experienced patients or any pediatric patients [see Dosage and Administration (2.2,2.3), Clinical Studies (14.2, 14.3)].
- Dosing of fosamprenavir calcium tablets plus ritonavir is not recommended for protease inhibitor-experienced pediatric patients younger than 6 months [see Clinical Pharmacology (12.3)].

2 DOSAGE AND ADMINISTRATION

2.1 General Dosing Information

Fosamprenavir calcium tablets may be taken with or without food.

Adults should take fosamprenavir calcium oral suspension without food. Pediatric patients should take fosamprenavir calcium oral suspension with food [see Clinical Pharmacology (12.3)]. If emesis occurs within 30 minutes after dosing, re-dosing of fosamprenavir calcium oral suspension should occur.

Higher-than-approved dose combinations of fosamprenavir calcium tablets plus ritonavir are not recommended due to an increased risk of transaminase elevations [see Overdosage (10)].

When fosamprenavir calcium tablets are used in combination with ritonavir, prescribers should consult the full prescribing information for ritonavir.

2.2 Adults

Therapy-Naive Adults

- Fosamprenavir calcium tablets 1,400 mg twice daily (without ritonavir).
- Fosamprenavir calcium tablets 1,400 mg once daily plus ritonavir 200 mg once daily.
- Fosamprenavir calcium tablets 1,400 mg once daily plus ritonavir 100 mg once daily.
  - Fosamprenavir calcium tablets 700 mg twice daily plus ritonavir 100 mg twice daily.

- Dosing of fosamprenavir calcium tablets 1,400 mg once daily plus ritonavir 100 mg once daily is supported by pharmacokinetic data [see Clinical Pharmacology (12.3)].

- Dosing of fosamprenavir calcium tablets 700 mg twice daily plus ritonavir 100 mg twice daily is supported by pharmacokinetic and safety data [see Clinical Pharmacology (12.3)].

Protease Inhibitor-Experienced Adults

- Fosamprenavir calcium tablets 700 mg twice daily plus ritonavir 100 mg twice daily.

Pregnancy

- Fosamprenavir calcium tablets 700 mg twice daily plus ritonavir 100 mg twice daily.
  - Dosing of fosamprenavir calcium tablets 700 mg twice daily plus ritonavir 100 mg twice daily should only be considered in pregnant patients who are already on a stable twice-daily regimen of fosamprenavir calcium /ritonavir 700 mg/100 mg prior to pregnancy and who are virologically suppressed (HIV-1 RNA less than 50 copies per mL). Lower exposures of amprenavir were observed during pregnancy; therefore, viral load should be monitored closely to ensure viral suppression is maintained [see Use in Specific Populations (8.1), Clinical Pharmacology (12.3)].Data regarding use of other regimens of fosamprenavir calcium tablets (with or without ritonavir) in pregnancy are not available.

2.3 Pediatric Patients (Aged at Least 4 Weeks to 18 Years)

The recommended dosage of fosamprenavir calcium in patients aged at least 4 weeks to 18 years should be calculated based on body weight (kg) and should not exceed the recommended adult dose (Table 1).

Table 1. Twice-Daily Dosage Regimens by Weight for Protease Inhibitor-Naive Pediatric Patients (Aged 4 Weeks and Older) and for Protease Inhibitor-Experienced Pediatric Patients (Aged 6 Months and Older) Using Fosamprenavir Calcium Oral Suspension with Concurrent Ritonavir

Weight | Twice-Daily Dosage Regimen
< 11 kg | Fosamprenavir Calcium 45 mg/kg plus ritonavir 7 mg/kga
11 kg - < 15 kg | Fosamprenavir Calcium 30 mg/kg plus ritonavir 3 mg/kga
15 kg - < 20 kg | Fosamprenavir Calcium 23 mg/kg plus ritonavir 3 mg/kga
≥ 20 kg | Fosamprenavir Calcium 18 mg/kg plus ritonavir 3 mg/kga

aWhen dosing with ritonavir, do not exceed the adult dose of fosamprenavir calcium 700 mg/ritonavir 100 mg twice-daily dose.

Alternatively, protease inhibitor-naive children aged 2 years and older can be administered fosamprenavir calcium (without ritonavir) 30 mg per kg twice daily.

Fosamprenavir calcium should only be administered to infants born at 38 weeks’ gestation or greater and who have attained a postnatal age of 28 days.

For pediatric patients, pharmacokinetic and clinical data:

- do not support once-daily dosing of fosamprenavir calcium alone or in combination with ritonavir [see Clinical Studies (14.3)].
- do not support administration of fosamprenavir calcium alone or in combination with ritonavir for protease inhibitor-experienced children younger than 6 months [see Clinical Pharmacology (12.3)].
- do not support twice-daily dosing of fosamprenavir calcium without ritonavir in pediatric patients younger than 2 years [see Clinical Pharmacology (12.3)].

Other Dosing Considerations

- When administered without ritonavir, the adult regimen of fosamprenavir calcium tablets 1,400 mg twice daily may be used for pediatric patients weighing at least 47 kg.
- When administered in combination with ritonavir, fosamprenavir calcium tablets may be used for pediatric patients weighing at least 39 kg; ritonavir capsules may be used for pediatric patients weighing at least 33 kg.

2.4 Patients with Hepatic Impairment

See Clinical Pharmacology (12.3).

Mild Hepatic Impairment (Child-Pugh Score Ranging from 5 to 6)

Fosamprenavir calcium tablets should be used with caution at a reduced dosage of 700 mg twice daily without ritonavir (therapy-naive) or 700 mg twice daily plus ritonavir 100 mg once daily (therapy-naive or protease inhibitor-experienced).

Moderate Hepatic Impairment (Child-Pugh Score Ranging from 7 to 9)

Fosamprenavir calcium tablets should be used with caution at a reduced dosage of 700 mg twice daily without ritonavir (therapy-naive) or 450 mg twice daily plus ritonavir 100 mg once daily (therapy-naive or protease inhibitor-experienced).

Severe Hepatic Impairment (Child-Pugh Score Ranging from 10 to 15)

Fosamprenavir calcium tablets should be used with caution at a reduced dosage of 350 mg twice daily without ritonavir (therapy-naive) or 300 mg twice daily plus ritonavir 100 mg once daily (therapy-naive or protease inhibitor-experienced).

There are no data to support dosing recommendations for pediatric patients with hepatic impairment.

3 DOSAGE FORMS AND STRENGTHS

Fosamprenavir calcium tablets, USP, 700 mg, are pink colored, coated, oval-shaped tablets with “ RJ47” imprinted on one side with black ink and plain on the other side.

4 CONTRAINDICATIONS

- Fosamprenavir calcium is contraindicated in patients with previously demonstrated clinically significant hypersensitivity (e.g., Stevens-Johnson syndrome) to any of the components of this product or to amprenavir.
- Fosamprenavir calcium is contraindicated when coadministered with drugs that are highly dependent on cytochrome P450 (CYP)3A4 for clearance and for which elevated plasma concentrations are associated with serious and/or life-threatening events. These drugs and other contraindicated drugs (which may lead to reduced efficacy of fosamprenavir calcium and possible resistance) are listed below [see Drug Interactions (7), Clinical Pharmacology (12.3)]. The list of contraindicated drugs applies to the use of fosamprenavir calcium with or without ritonavir, unless otherwise indicated. If fosamprenavir calcium is coadministered with ritonavir, reference should be made to the full prescribing information for ritonavir for additional contraindications.
- Fosamprenavir calcium is contraindicated when coadministered with the following drugs:
  - Alpha 1-adrenoreceptor antagonist: Alfuzosin
  - Antiarrhythmics: Flecainide (with ritonavir), propafenone (with ritonavir)
  - Antimycobacterial: Rifampin
  - Antipsychotic: Lurasidone (with ritonavir), pimozide
  - Ergot derivatives: Dihydroergotamine, ergonovine, ergotamine, methylergonovine
  - GI motility agent: Cisapride
  - Herbal product: St. John’s wort (Hypericum perforatum)
  - Lipid modifying agents: Lomitapide, lovastatin, simvastatin
  - Non-nucleoside reverse transcriptase inhibitor: Delavirdine
  - PDE5 inhibitor: Sildenafil (Revatio) (for treatment of pulmonary arterial hypertension)
  - Sedative/hypnotics: Midazolam, triazolam

5 WARNINGS AND PRECAUTIONS

5.1 Risk of Serious Adverse Reactions Due to Drug Interactions

Initiation of fosamprenavir calcium/ritonavir, a CYP3A inhibitor, in patients receiving medications metabolized by CYP3A, or initiation of medications metabolized by CYP3A in patients already receiving fosamprenavir calcium/ritonavir may increase plasma concentrations of medications metabolized by CYP3A. Initiation of medications that inhibit or induce CYP3A may increase or decrease concentrations of fosamprenavir calcium/ritonavir, respectively. These interactions may lead to:

- clinically significant adverse reactions, potentially leading to severe, life-threatening, or fatal events from greater exposures of concomitant medications.
- clinically significant adverse reactions from greater exposures of fosamprenavir calcium/ritonavir.
- loss of therapeutic effect of fosamprenavir calcium/ritonavir and possible development of resistance.

See Table 6 for steps to prevent or manage these possible and known significant drug interactions, including dosing recommendations [see Drug Interactions (7)]. Consider the potential for drug interactions prior to and during therapy with fosamprenavir calcium/ritonavir; review concomitant medications during therapy with fosamprenavir calcium/ritonavir, and monitor for the adverse reactions associated with the concomitant medications [see Contraindications (4), Drug Interactions (7)].

5.2 Skin Reactions

Severe and life-threatening skin reactions, including 1 case of Stevens-Johnson syndrome among 700 subjects treated with fosamprenavir calcium in clinical trials. Treatment with fosamprenavir calcium should be discontinued for severe or life-threatening rashes and for moderate rashes accompanied by systemic symptoms [see Adverse Reactions (6)].

5.3 Sulfa Allergy

Fosamprenavir calcium should be used with caution in patients with a known sulfonamide allergy. Fosamprenavir contains a sulfonamide moiety. The potential for cross-sensitivity between drugs in the sulfonamide class and fosamprenavir is unknown. In a clinical trial of fosamprenavir calcium used as the sole protease inhibitor, rash occurred in 2 of 10 subjects (20%) with a history of sulfonamide allergy compared with 42 of 126 subjects (33%) with no history of sulfonamide allergy. In 2 clinical trials of fosamprenavir calcium plus low-dose ritonavir, rash occurred in 8 of 50 subjects (16%) with a history of sulfonamide allergy compared with 50 of 412 subjects (12%) with no history of sulfonamide allergy.

5.4 Hepatic Toxicity

Use of fosamprenavir calcium with ritonavir at higher-than-recommended dosages may result in transaminase elevations and should not be used [see Dosage and Administration (2), Overdosage (10)]. Patients with underlying hepatitis B or C or marked elevations in transaminases prior to treatment may be at increased risk for developing or worsening of transaminase elevations. Appropriate laboratory testing should be conducted prior to initiating therapy with fosamprenavir calcium and patients should be monitored closely during treatment.

5.5 Diabetes/Hyperglycemia

New onset diabetes mellitus, exacerbation of pre-existing diabetes mellitus, and hyperglycemia have been reported during postmarketing surveillance in HIV-1-infected patients receiving protease inhibitor therapy. Some patients required either initiation or dose adjustments of insulin or oral hypoglycemic agents for treatment of these events. In some cases, diabetic ketoacidosis has occurred. In those patients who discontinued protease inhibitor therapy, hyperglycemia persisted in some cases. Because these events have been reported voluntarily during clinical practice, estimates of frequency cannot be made and causal relationships between protease inhibitor therapy and these events have not been established.

5.6 Immune Reconstitution Syndrome

Immune reconstitution syndrome has been reported in patients treated with combination antiretroviral therapy, including fosamprenavir calcium. During the initial phase of combination antiretroviral treatment, patients whose immune systems respond may develop an inflammatory response to indolent or residual opportunistic infections (such as Mycobacterium aviuminfection, cytomegalovirus, Pneumocystis jiroveciipneumonia [PCP], or tuberculosis), which may necessitate further evaluation and treatment.

Autoimmune disorders (such as Graves’ disease, polymyositis, and Guillain-Barré syndrome) have also been reported to occur in the setting of immune reconstitution; however, the time to onset is more variable, and can occur many months after initiation of treatment.

5.7 Increase in Body Fat

Increase of body fat has been observed in patients receiving protease inhibitors, including fosamprenavir calcium. The mechanism and long-term consequences of these events are currently unknown. A causal relationship has not been established.

5.8 Lipid Elevations

Treatment with fosamprenavir calcium plus ritonavir has resulted in increases in the concentration of triglycerides and cholesterol [see Adverse Reactions (6)]. Triglyceride and cholesterol testing should be performed prior to initiating therapy with fosamprenavir calcium and at periodic intervals during therapy. Lipid disorders should be managed as clinically appropriate [see Drug Interactions (7)].

5.9 Hemolytic Anemia

Acute hemolytic anemia has been reported in a patient treated with amprenavir.

5.10 Patients with Hemophilia

There have been reports of spontaneous bleeding in patients with hemophilia A and B treated with protease inhibitors. In some patients, additional factor VIII was required. In many of the reported cases, treatment with protease inhibitors was continued or restarted. A causal relationship between protease inhibitor therapy and these episodes has not been established.

5.11 Nephrolithiasis

Cases of nephrolithiasis were reported during postmarketing surveillance in HIV-1-infected patients receiving fosamprenavir calcium. Because these events were reported voluntarily during clinical practice, estimates of frequency cannot be made. If signs or symptoms of nephrolithiasis occur, temporary interruption or discontinuation of therapy may be considered.

5.12 Resistance/Cross-Resistance

Because the potential for HIV cross-resistance among protease inhibitors has not been fully explored, it is unknown what effect therapy with fosamprenavir calcium will have on the activity of subsequently administered protease inhibitors. Fosamprenavir calcium has been studied in patients who have experienced treatment failure with protease inhibitors [see Clinical Studies (14.2)].

6 ADVERSE REACTIONS

- Severe or life-threatening skin reactions have been reported with the use of fosamprenavir calcium [see Warnings and Precautions (5.2)].
- The most common moderate to severe adverse reactions in clinical trials of fosamprenavir calcium were diarrhea, rash, nausea, vomiting, and headache.
- Treatment discontinuation due to adverse events occurred in 6.4% of subjects receiving fosamprenavir calcium and in 5.9% of subjects receiving comparator treatments. The most common adverse reactions leading to discontinuation of fosamprenavir calcium (incidence less than or equal to 1% of subjects) included diarrhea, nausea, vomiting, AST increased, ALT increased, and rash.

6.1 Clinical Trials Experience

Because clinical trials are conducted under widely varying conditions, adverse reaction rates observed in the clinical trials of a drug cannot be directly compared with rates in the clinical trials of another drug and may not reflect the rates observed in clinical practice.

Adult Trials

The data for the 3 active-controlled clinical trials described below reflect exposure of 700 HIV-1-infected subjects to fosamprenavir calcium tablets, including 599 subjects exposed to fosamprenavir calcium for greater than 24 weeks, and 409 subjects exposed for greater than 48 weeks. The population age ranged from 17 to 72 years. Of these subjects, 26% were female, 51% white, 31% black, 16% American Hispanic, and 70% were antiretroviral-naive. Sixty-one percent received fosamprenavir calcium 1,400 mg once daily plus ritonavir 200 mg once daily; 24% received fosamprenavir calcium 1,400 mg twice daily; and 15% received fosamprenavir calcium 700 mg twice daily plus ritonavir 100 mg twice daily.

Selected adverse reactions reported during the clinical efficacy trials of fosamprenavir calcium are shown in Tables 2 and 3. Each table presents adverse reactions of moderate or severe intensity in subjects treated with combination therapy for up to 48 weeks.

Table 2. Selected Moderate/Severe Clinical Adverse Reactions Reported in Greater than or Equal to 2% of Antiretroviral-Naive Adult Subjects

Adverse Reaction | APV30001a |  | APV30002a
Adverse Reaction | Fosamprenavir Calcium 1,400 mg Twice Daily; (n = 166) | Nelfinavir; 1,250 mg; Twice Daily (n = 83) | Fosamprenavir Calcium 1,400 mg; and; Ritonavir 200 mg Once Daily; (n = 322) | Nelfinavir; 1,250 mg Twice Daily; (n = 327)
Gastrointestinal
Diarrhea | 5% | 18% | 10% | 18%
Nausea | 7% | 4% | 7% | 5%
Vomiting | 2% | 4% | 6% | 4%
Abdominal pain | 1% | 0% | 2% | 2%
Skin
Rash | 8% | 2% | 3% | 2%
General disorders
Fatigue | 2% | 1% | 4% | 2%
Nervous system
Headache | 2% | 4% | 3% | 3%

aAll subjects also received abacavir and lamivudine twice daily.

Table 3. Selected Moderate/Severe Clinical Adverse Reactions Reported in Greater than or Equal to 2% of Protease Inhibitor-Experienced Adult Subjects (Trial APV30003)

Adverse Reaction | Fosamprenavir Calcium 700 mg and Ritonavir 100 mg Twice Dailya; (n = 106) | Lopinavir 400 mg and; Ritonavir 100 mg Twice Dailya; (n = 103)
Gastrointestinal
Diarrhea | 13% | 11%
Nausea | 3% | 9%
Vomiting | 3% | 5%
Abdominal pain | < 1% | 2%
Skin
Rash | 3% | 0%
Nervous system
Headache | 4% | 2%

aAll subjects also received 2 reverse transcriptase inhibitors.

Skin rash (without regard to causality) occurred in approximately 19% of subjects treated with fosamprenavir calcium in the pivotal efficacy trials. Rashes were usually maculopapular and of mild or moderate intensity, some with pruritus. Rash had a median onset of 11 days after initiation of fosamprenavir calcium and had a median duration of 13 days. Skin rash led to discontinuation of fosamprenavir calcium in less than 1% of subjects. In some subjects with mild or moderate rash, dosing with fosamprenavir calcium was often continued without interruption; if interrupted, reintroduction of fosamprenavir calcium generally did not result in rash recurrence.

The percentages of subjects with Grade 3 or 4 laboratory abnormalities in the clinical efficacy trials of fosamprenavir calcium are presented in Tables 4 and 5.

Table 4. Grade 3/4 Laboratory Abnormalities Reported in Greater than or Equal to 2% of Antiretroviral-Naive Adult Subjects in Trials APV30001 and APV30002

Laboratory Abnormality | APV30001a |  | APV30002a
Laboratory Abnormality | Fosamprenavir Calcium 1,400 mg Twice Daily; (n = 166) | Nelfinavir; 1,250 mg Twice Daily; (n = 83) | Fosamprenavir Calcium 1,400 mg and Ritonavir 200 mg Once Daily; (n = 322) | Nelfinavir; 1,250 mg Twice Daily; (n = 327)
ALT (> 5 x ULN) | 6% | 5% | 8% | 8%
AST (> 5 x ULN) | 6% | 6% | 6% | 7%
Serum lipase (> 2 x ULN) | 8% | 4% | 6% | 4%
Triglyceridesb(> 750 mg/dL) | 0% | 1% | 6% | 2%
Neutrophil count, absolute (< 750 cells/mm^3) | 3% | 6% | 3% | 4%

aAll subjects also received abacavir and lamivudine twice daily.

bFasting specimens.

ULN = Upper limit of normal.

The incidence of Grade 3 or 4 hyperglycemia in antiretroviral-naive subjects who received fosamprenavir calcium in the pivotal trials was less than 1%.

Table 5. Grade 3/4 Laboratory Abnormalities Reported in Greater than or Equal to 2% of Protease Inhibitor-Experienced Adult Subjects in Trial APV30003

Laboratory Abnormality | Fosamprenavir Calcium 700 mg and Ritonavir 100 mg Twice Dailya; (n = 104) | Lopinavir 400 mg and; Ritonavir 100 mg Twice Dailya; (n = 103)
Triglyceridesb(> 750 mg/dL) | 11%c | 6%c
Serum lipase (> 2 x ULN) | 5% | 12%
ALT (> 5 x ULN) | 4% | 4%
AST (> 5 x ULN) | 4% | 2%
Glucose (> 251 mg/dL) | 2%c | 2%c

aAll subjects also received 2 reverse transcriptase inhibitors.

bFasting specimens.

cn = 100 for fosamprenavir calcium plus ritonavir, n = 98 for lopinavir plus ritonavir.

ULN = Upper limit of normal.

Pediatric Trials

Fosamprenavir calcium with and without ritonavir was studied in 237 HIV-1-infected pediatric subjects aged at least 4 weeks to 18 years in 3 open-label trials; APV20002, APV20003, and APV29005 [see Clinical Studies (14.3)]. Vomiting and neutropenia occurred more frequently in pediatric subjects compared with adults. Other adverse events occurred with similar frequency in pediatric subjects compared with adults.

The frequency of vomiting among pediatric subjects receiving fosamprenavir calcium twice daily with ritonavir was 20% in subjects aged at least 4 weeks to younger than 2 years and 36% in subjects aged 2 to 18 years compared with 10% in adults. The frequency of vomiting among pediatric subjects receiving fosamprenavir calcium twice daily without ritonavir was 60% in subjects aged 2 to 5 years compared with 16% in adults.

The median duration of drug-related vomiting episodes in APV29005 was 1 day (range: 1 to 3 days), in APV20003 was 16 days (range: 1 to 38 days), and in APV20002 was 9 days (range: 4 to 13 days). Vomiting was treatment limiting in 4 pediatric subjects across all 3 trials.

The incidence of Grade 3 or 4 neutropenia (neutrophils less than 750 cells per mm^3) seen in pediatric subjects treated with fosamprenavir calcium with and without ritonavir was higher (15%) than the incidence seen in adult subjects (3%). Grade 3/4 neutropenia occurred in 10% (5 of 51) of subjects aged at least 4 weeks to younger than 2 years and 16% (28 of 170) of subjects aged 2 to 18 years.

6.2 Postmarketing Experience

The following adverse reactions have been identified during postapproval use of fosamprenavir calcium. Because these reactions are reported voluntarily from a population of unknown size, it is not always possible to reliably estimate their frequency or establish a causal relationship to drug exposure.

These reactions have been chosen for inclusion due to a combination of their seriousness, frequency of reporting, or potential causal connection to fosamprenavir calcium.

Cardiac Disorders

Myocardial infarction.

Metabolism and Nutrition Disorders

Hypercholesterolemia.

Nervous System Disorders

Oral paresthesia.

Skin and Subcutaneous Tissue Disorders

Angioedema.

Urogenital

Nephrolithiasis.

7 DRUG INTERACTIONS

7.1 Cytochrome P450 Inhibitors and Inducers

Amprenavir, the active metabolite of fosamprenavir, is an inhibitor of CYP3A4 metabolism and therefore should not be administered concurrently with medications with narrow therapeutic windows that are substrates of CYP3A4. Data also suggest that amprenavir induces CYP3A4.

Amprenavir is metabolized by CYP3A4. Coadministration of fosamprenavir calcium and drugs that induce CYP3A4, such as rifampin, may decrease amprenavir concentrations and reduce its therapeutic effect. Coadministration of fosamprenavir calcium and drugs that inhibit CYP3A4 may increase amprenavir concentrations and increase the incidence of adverse effects.

The potential for drug interactions with fosamprenavir calcium changes when fosamprenavir calcium is coadministered with the potent CYP3A4 inhibitor ritonavir. The magnitude of CYP3A4-mediated drug interactions (effect on amprenavir or effect on coadministered drug) may change when fosamprenavir calcium is coadministered with ritonavir. Because ritonavir is a CYP2D6 inhibitor, clinically significant interactions with drugs metabolized by CYP2D6 are possible when coadministered with fosamprenavir calcium plus ritonavir. Ritonavir also appears to induce CYP3A, CYP1A2, CYP2C9, CYP2C19, and CYP2B6, as well as other enzymes, including glucuronosyl transferase.

There are other agents that may result in serious and/or life-threatening drug interactions [see Contraindications (4)].

7.2 Established and Other Potentially Significant Drug Interactions

If fosamprenavir calcium is used in combination with ritonavir, see full prescribing information for ritonavir for additional information on drug interactions [see Contraindications (4), Clinical Pharmacology (12.3)].

Table 6 provides a listing of established or potentially clinically significant drug interactions. Information in the table applies to fosamprenavir calcium with or without ritonavir, unless otherwise indicated.

Table 6. Established and Other Potentially Significant Drug Interactions

Concomitant Drug Class: Drug Name | Effect on Concentration of Amprenavir or Concomitant Drug | Clinical Comment
HCV/HIV-Antiviral Agents
HCV protease inhibitor:; Boceprevir | Fosamprenavir calcium:; ↓ Amprenavir; (predicted); ↔ or ↓ Boceprevir; (predicted); Fosamprenavir calcium /ritonavir:; ↓Amprenavir; (predicted); ↓Boceprevir; (predicted) | Coadministration of fosamprenavir calcium or fosamprenavir calcium/ ritonavir and boceprevir is not recommended.
HCV protease inhibitor:; Simeprevir | Fosamprenavir calcium:; ↔ Amprenavir; (predicted); ↑ or ↓ Simeprevir; (predicted); Fosamprenavir calcium /ritonavir:; ↔Amprenavir; (predicted); ↑Simeprevir; (predicted) | Coadministration of fosamprenavir calcium or fosamprenavir calcium/ritonavir and simeprevir is not recommended.
HCV protease inhibitor:; Paritaprevir (coformulated with ritonavir and ombitasvir and coadministered with dasabuvir) | Fosamprenavir calcium:; ↑Amprenavir; (predicted); ↑ or ↔Paritaprevir; (predicted); Fosamprenavir calcium /ritonavir:; ↑ or ↔Amprenavir; (predicted); ↑Paritaprevir; (predicted) | Appropriate doses of the combinations with respect to safety and efficacy have not been established.; Fosamprenavircalcium 1,400 mg once daily may be considered when coadministered with paritaprevir/ritonavir/ombitasvir/ dasabuvir.; Coadministration of Fosamprenavircalcium /ritonavir and paritaprevir/ritonavir/ombitasvir/ dasabuvir is not recommended.
Non-nucleoside reverse transcriptase inhibitor:; Delavirdinea | Fosamprenavir calcium:; ↑ Amprenavir; ↓ Delavirdine | Coadministration is contraindicated as it may lead to loss of virologic response and possible resistance to delavirdine [see Contraindications (4)].
Non-nucleoside reverse transcriptase inhibitor:; Delavirdinea | Fosamprenavir calcium/ritonavir:; ↑ Amprenavir; ↓Delavirdine | Coadministration is contraindicated as it may lead to loss of virologic response and possible resistance to delavirdine [see Contraindications (4)].
Non-nucleoside reverse transcriptase inhibitor:; Efavirenza | Fosamprenavir calcium:; ↓ Amprenavir; Fosamprenavir calcium/ritonavir:; ↓ Amprenavir | Appropriate doses of the combinations with respect to safety and efficacy have not been established.; An additional 100 mg/day (300 mg total) of ritonavir is recommended when efavirenz is administered with fosamprenavir calcium /ritonavir once daily. No change in the ritonavir dose is required when efavirenz is administered with Fosamprenavir calcium plus ritonavir twice daily.
Non-nucleoside reverse transcriptase inhibitor:Nevirapinea | Fosamprenavir calcium:; ↓ Amprenavir; ↑ Nevirapine | Coadministration of nevirapine and fosamprenavir calcium without ritonavir is not recommended.
Non-nucleoside reverse transcriptase inhibitor:Nevirapinea | Fosamprenavir calcium/ritonavir:; ↓ Amprenavir; ↑ Nevirapine | No dosage adjustment required when nevirapine is administered with fosamprenavir calcium/ritonavir twice daily.
Non-nucleoside reverse transcriptase inhibitor:Nevirapinea |  | The combination of nevirapine administered with fosamprenavir calcium/ritonavir once-daily regimen has not been studied.
HIV protease inhibitor:; Atazanavira | Fosamprenavir calcium:; Interaction has not been evaluated. | Appropriate doses of the combinations with respect to safety and efficacy have not been established.
HIV protease inhibitor:; Atazanavira | Fosamprenavir calcium/ritonavir:; ↓ Atazanavir; ↔ Amprenavir
HIV protease inhibitors:; Indinavira, nelfinavira | Fosamprenavir calcium:; ↑ Amprenavir; Effect on indinavir and nelfinavir is not well established.; Fosamprenavir calcium/ritonavir:Interaction has not been evaluated. | Appropriate doses of the combinations with respect to safety and efficacy have not been established.
HIV protease inhibitors:Lopinavir/ritonavira | ↓ Amprenavir; ↓ Lopinavir | An increased rate of adverse events has been observed. Appropriate doses of the combinations with respect to safety and efficacy have not been established.
HIV protease inhibitor:; Saquinavira | Fosamprenavir calcium:; ↓ Amprenavir; Effect on saquinavir; is not well established.; Fosamprenavir calcium/ritonavir:Interaction has not been evaluated. | Appropriate doses of the combination with respect to safety and efficacy have not been established.
HIV integrase inhibitor:; Raltegravira | Fosamprenavir calcium:; ↓ Amprenavir; ↓ Raltegravir; Fosamprenavir calcium/ritonavir:; ↓ Amprenavir; ↓ Raltegravir | Appropriate doses of the combination with respect to safety and efficacy have not been established.
HIV integrase inhibitor:Dolutegravira | Fosamprenavir calcium /ritonavir:↓Dolutegravir | The recommended dose of dolutegravir is 50 mg twice daily when coadministered with Fosamprenavircalcium /ritonavir.; Use an alternative combination where possible in patients with known or suspected integrase inhibitor resistance.
HIV CCR5 co-receptor antagonist:; Maraviroca | Fosamprenavir calcium/ritonavir:; ↓ Amprenavir; ↑ Maraviroc | No dosage adjustment required for fosamprenavir calcium /ritonavir. The recommended dose of maraviroc is 150 mg twice daily when coadministered with fosamprenavir calcium/ritonavir. Fosamprenavir calcium should be given with ritonavir when coadministered with maraviroc.
Other Agents
Alpha 1-adrenoreceptor antagonist:; Alfuzosin | ↑Alfuzosin | Coadministration is contraindicated due to potential hypotension [see Contraindications (4)].
Antacid:; MAALOX TC | ↓Amprenavir | Use with caution when administered at the same time. Fosamprenavir calcium may be less effective due to decreased amprenavir plasma concentrations.; Staggered coadministration of antacids and fosamprenavir calcium has not been evaluated.
Antiarrhythmics:; Amiodarone, disopyramide, lidocaine (systemic), and quinidine; Flecainide, propafenone | ↑ Antiarrhythmics; ↑Antiarrhythmics | Therapeutic concentration monitoring, if available, is recommended for antiarrhythmics.; Coadministration is contraindicated due to potential for serious and/or life-threatening reactions such as cardiac arrhythmias if fosamprenavir calcium is co-prescribed with ritonavir [see Contraindications (4)].
Anticoagulant:; Warfarin |  | Concentrations of warfarin may be affected. It is recommended that INR (international normalized ratio) be monitored.
Anticonvulsants:; Carbamazepine,; phenobarbital, phenytoin | Fosamprenavir calcium:; ↓ Amprenavir | Use with caution. Fosamprenavir calcium may be less effective due to decreased amprenavir plasma concentrations in patients taking these agents concomitantly.
Phenytoina | Fosamprenavir calcium/ritonavir:; ↑ Amprenavir; ↓ Phenytoin | Plasma phenytoin concentrations should be monitored and phenytoin dose should be increased as appropriate. No change in fosamprenavir calcium/ritonavir dose is recommended.
Antidepressant:; Paroxetine, trazodone | ↓ Paroxetine | Any paroxetine dose adjustment should; be guided by clinical effect (tolerability and efficacy).
 | ↑ Trazodone | Adverse events of nausea, dizziness, hypotension, and syncope have been observed following coadministration of trazodone and ritonavir. If trazodone is used with a CYP3A4 inhibitor such as fosamprenavir calcium, the combination should be used with caution and a lower dose of trazodone should be considered.
Antifungals:; Ketoconazolea,; itraconazole | ↑ Ketoconazole; ↑ Itraconazole | Increase monitoring for adverse events.; Fosamprenavir calcium:; Dose reduction of ketoconazole or itraconazole may be needed for patients receiving more than 400 mg ketoconazole or itraconazole per day.; Fosamprenavir calcium/ritonavir:; High doses of ketoconazole or itraconazole (greater than 200 mg/day) are not recommended.
Anti-gout:; Colchicine | ↑ Colchicine | Patients with renal or hepatic impairment should not be given colchicine with fosamprenavir calcium/ritonavir.; Fosamprenavir calcium/ritonavir and coadministration of colchicine:; Treatment of gout flares:; 0.6 mg (1 tablet) x 1 dose, followed by 0.3 mg (half tablet) 1 hour later. Dose to be repeated no earlier than 3 days.; Prophylaxis of gout flares:; If the original regimen was 0.6 mg twice a day, the regimen should be adjusted to 0.3 mg once a day. If the original regimen was 0.6 mg once a day, the regimen should be adjusted to 0.3 mg once every other day.; Treatment of familial Mediterranean fever (FMF):; Maximum daily dose of 0.6 mg (may be given as 0.3 mg twice a day).; Fosamprenavir calcium and coadministration of colchicine:; Treatment of gout flares:; 1.2 mg (2 tablets) x 1 dose. Dose to be repeated no earlier than 3 days.; Prophylaxis of gout flares:; If the original regimen was 0.6 mg twice a day, the regimen should be adjusted to 0.3 mg twice a day or 0.6 mg once a day.; If the original regimen was 0.6 mg once a day, the regimen should be adjusted to 0.3 mg once a day.; Treatment of FMF:; Maximum daily dose of 1.2 mg (may be given as 0.6 mg twice a day).
Antimycobacterial:; Rifabutina | ↑ Rifabutin and rifabutin metabolite | A complete blood count should be performed weekly and as clinically indicated to monitor for neutropenia.; Fosamprenavir calcium:; A dosage reduction of rifabutin by at least half the recommended dose is required.; Fosamprenavir calcium/ritonavir:; Dosage reduction of rifabutin by at least 75% of the usual dose of 300 mg/day is recommended (a maximum dose of 150 mg every other day or 3 times per week).
Antimycobacterial:Rifampina | ↓Amprenavir | Coadministration is contraindicated as it may lead to loss of virologic response and possible resistance to Fosamprenavir calcium or to the class of protease inhibitors [see Contraindications (4)].
Antineoplastics:Dasatinib, nilotinib, ibrutinib, vinblastine, everolimus | ↑Antineoplastics | Fosamprenavir calcium or fosamprenavir calcium /ritonavir may increase plasma concentrations of antineoplastics metabolized by CYP3A, potentially increasing the risk of adverse events typically associated with these medications. In case of coadministration, please refer to relevant prescribing information for these medications.
Antipsychotics:; Lurasidone; Pimozide; Quetiapine | ↑Lurasidone; ↑Pimozide; ↑Quetiapine | Fosamprenavir calcium:; If coadministration is necessary, reduce the lurasidone dose. Refer to the lurasidone prescribing information for concomitant use with moderate CYP3A4 inhibitors.; Fosamprenavir calcium /ritonavir:; Use of lurasidone is contraindicated due to potential for serious and/or life-threatening reactions [see Contraindications (4)].; Coadministration is contraindicated due to potential for serious and/or life-threatening reactions such as cardiac arrhythmias [see Contraindications (4)].; Fosamprenavir calcium /ritonavir:; Initiation of fosamprenavir calcium with ritonavir in patients taking quetiapine: Consider alternative antiretroviral therapy to avoid increases in quetiapine drug exposures. If coadministration is necessary, reduce the quetiapine dose to 1/6 of the current dose and monitor for quetiapine-associated adverse reactions. Refer to the quetiapine prescribing information for recommendations on adverse reaction monitoring.; Initiation of quetiapine in patients taking fosamprenavir calcium with ritonavir: Refer to the quetiapine prescribing information for initial dosing and titration of quetiapine.
Benzodiazepines:; Alprazolam, clorazepate, diazepam, flurazepam | ↑ Benzodiazepines | Clinical significance is unknown. A decrease in benzodiazepine dose may be needed.
Calcium channel blockers:; Diltiazem, felodipine, nifedipine, nicardipine, nimodipine, verapamil, amlodipine, nisoldipine, isradipine | ↑ Calcium channel blockers | Use with caution. Clinical monitoring of patients is recommended.
Corticosteroid:Dexamethasone | ↓ Amprenavir | Use with caution. Fosamprenavir calcium may be less effective due to decreased amprenavir plasma concentrations.
Endothelin-receptor antagonist:; Bosentan | ↑ Bosentan | Coadministration of bosentan in patients on fosamprenavir calcium:; In patients who have been receiving fosamprenavir calcium for at least 10 days, start bosentan at 62.5 mg once daily or every other day based upon individual tolerability.; Coadministration of fosamprenavir calcium in patients on bosentan:; Discontinue use of bosentan at least 36 hours prior to initiation of fosamprenavir calcium.After at least 10 days following the initiation of fosamprenavir calcium, resume bosentan at 62.5 mg once daily or every other day based upon individual tolerability.
Ergot derivatives:; Dihydroergotamine,; ergonovine, ergotamine,; methylergonovine | ↑Ergot derivatives | Coadministration is contraindicated due to potential for serious and/or life-threatening reactions such as acute ergot toxicity characterized by peripheral vasospasm and ischemia of the extremities and other tissues [see Contraindications (4)].
GI motility agent:; Cisapride | ↑Cisapride | Coadministration is contraindicated due to potential for serious and/or life-threatening reactions such as cardiac arrhythmias [see Contraindications (4)].
Herbal product:; St. John’s wort; (Hypericum perforatum) | ↓Amprenavir | Coadministration is contraindicated as it may lead to loss of virologic response and possible resistance to Fosamprenavir calcium or to the class of protease inhibitors [see Contraindications (4)].
Histamine H2-receptor antagonists:; Cimetidine, famotidine, nizatidine, ranitidinea | Fosamprenavir calcium:; ↓ Amprenavir; Fosamprenavir calcium/ritonavir:; Interaction not evaluated | Use with caution. Fosamprenavir calcium may be less effective due to decreased amprenavir plasma concentrations.
Immunosuppressants:; Cyclosporine, tacrolimus,; sirolimus | ↑ Immunosuppressants | Therapeutic concentration monitoring is recommended for immunosuppressant agents.
Inhaled beta-agonist:; Salmeterol | ↑ Salmeterol | Concurrent administration of salmeterol with fosamprenavir calcium is not recommended. The combination may result in increased risk of cardiovascular adverse events associated with salmeterol, including QT prolongation, palpitations, and sinus tachycardia.
Inhaled/nasal steroid:; Fluticasone | Fosamprenavir calcium:; ↑ Fluticasone | Use with caution. Consider alternatives to fluticasone, particularly for long-term use.
 | Fosamprenavir calcium/ritonavir:; ↑ Fluticasone | May result in significantly reduced serum cortisol concentrations. Systemic corticosteroid effects including Cushing’s syndrome and adrenal suppression have been reported during postmarketing use in patients receiving ritonavir and inhaled or intranasally administered fluticasone. Coadministration of fluticasone and fosamprenavir calcium/ritonavir is not recommended unless the potential benefit to the patient outweighs the risk of systemic corticosteroid side effects.
Lipid Modifying Agents: HMG-CoA reductase inhibitors:; Atorvastatina; Lovastatin, simvastatin; Other lipid modifying agents:; Lomitapide | ↑Atorvastatin; ↑Lovastatin; ↑Simvastatin; ↑Lomitapide | Titrate atorvastatin dose carefully and use the lowest necessary dose; do not exceed atorvastatin 20 mg/day.; Coadministration with lovastatin or simvastatin is contraindicated due to potential for serious reactions such as risk of myopathy including rhabdomyolysis [see Contraindications (4)].; Coadministration with lomitapide is contraindicated due to potential for markedly increased transaminases.
Narcotic analgesic:; Methadone; Fentanyl | ↓ Methadone; ↑Fentanyl | Data suggest that the interaction is not clinically relevant; however, patients should be monitored for opiate withdrawal symptoms.; Careful monitoring of therapeutic effects and adverse effects of fentanyl (including potentially fatal respiratory depression) is recommended.
Oral contraceptives:; Ethinyl estradiol/norethindronea |  | Alternative methods of non-hormonal contraception are recommended.
Oral contraceptives:; Ethinyl estradiol/norethindronea | Fosamprenavir calcium:; ↓ Amprenavir; ↓ Ethinyl estradiol | May lead to loss of virologic response.a
Oral contraceptives:; Ethinyl estradiol/norethindronea | Fosamprenavir calcium/ritonavir:; ↓ Ethinyl estradiol | Increased risk of transaminase elevations. No data are available on the use of fosamprenavir calcium/ritonavir with other hormonal therapies, such as hormone replacement therapy (HRT) for postmenopausal women.
PDE5 inhibitors:; Sildenafil, tadalafil,; vardenafil | ↑ Sildenafil; ↑ Tadalafil; ↑ Vardenafil | May result in an increase in PDE5 inhibitor-associated adverse events, including hypotension, syncope, visual disturbances, and priapism.; Use of PDE5 inhibitors for pulmonary arterial hypertension (PAH):; •Use of sildenafil (REVATIO) is contraindicated when used for the treatment of PAH. A safe and effective dose has not been established when used with fosamprenavir calcium. There is increased potential for sildenafil-associated adverse events (which include visual disturbances, hypotension, prolonged erection, and syncope) [see Contraindications (4)].• The following dose adjustments are recommended for use of tadalafil (ADCIRCA®) with fosamprenavir calcium: Coadministration of ADCIRCA in patients on fosamprenavir calcium:In patients receiving fosamprenavir calcium for at least one week, start ADCIRCA at 20 mg once daily. Increase to 40 mg once daily based upon individual tolerability. Coadministration of fosamprenavir calcium in patients on ADCIRCA:Avoid use of ADCIRCA during the initiation of fosamprenavir calcium. Stop ADCIRCA at least 24 hours prior to starting fosamprenavir calcium. After at least one week following the initiation of fosamprenavir calcium, resume ADCIRCA at 20 mg once daily. Increase to 40 mg once daily based upon individual tolerability.; Use of PDE5 inhibitors for erectile dysfunction:; Fosamprenavir calcium:; Sildenafil: 25 mg every 48 hours.; Tadalafil: no more than 10 mg every 72 hours.; Vardenafil: no more than 2.5 mg every 24 hours.; Fosamprenavir calcium/ritonavir:; Sildenafil: 25 mg every 48 hours.; Tadalafil: no more than 10 mg every 72 hours.; Vardenafil: no more than 2.5 mg every 72 hours.; Use with increased monitoring for adverse events.
Proton pump inhibitors:; Esomeprazolea, lansoprazole, omeprazole, pantoprazole, rabeprazole | Fosamprenavir calcium:; ↔ Amprenavir; ↑ Esomeprazole | Proton pump inhibitors can be administered at the same time as a dose of fosamprenavir calcium with no change in plasma amprenavir concentrations.
 | Fosamprenavir calcium/ritonavir:; ↔ Amprenavir; ↔ Esomeprazole
Sedative/hypnotics:; Midazolam, triazolam | ↑Midazolam; ↑Triazolam | Coadministration is contraindicated due to potential for serious and/or life-threatening reactions such as prolonged or increased sedation or respiratory depression [see Contraindications (4)].
Tricyclic antidepressants:; Amitriptyline, imipramine | ↑ Tricyclics | Therapeutic concentration monitoring is recommended for tricyclic antidepressants.

a See Clinical Pharmacology (12.3) Tables 10, 11, 12, or 13 for magnitude of interaction.

8 USE IN SPECIFIC POPULATIONS

8.1 Pregnancy

Pregnancy Exposure Registry

There is a pregnancy exposure registry that monitors pregnancy outcomes in women exposed to fosamprenavir calcium during pregnancy. Healthcare providers are encouraged to register patients by calling the Antiretroviral Pregnancy Registry (APR) at 1-800-258-4263.

Risk Summary

Limited data are available for use of fosamprenavir calcium in pregnancy. fosamprenavir calcium 700 mg twice daily taken with ritonavir 100 mg twice daily should only be considered in pregnant patients who are already on a stable twice-daily regimen of fosamprenavir calcium/ritonavir 700 mg/100 mg prior to pregnancy, and who are virologically suppressed (HIV-1 RNA less than 50 copies per mL) (see Clinical Considerations and Data).

There are insufficient human data on the use of fosamprenavir during pregnancy to adequately assess a drug-associated risk for birth defects and miscarriage. Given the limited number of pregnancies exposed to fosamprenavir-based regimens, no conclusions can be drawn on the safety of fosamprenavir in pregnancy. The background risk for major birth defects and miscarriage for the indicated population is unknown. The background rate for major birth defects in a U.S. reference population of the Metropolitan Atlanta Congenital Defects Program (MACDP) is 2.7% (see Data). The estimated background rate of miscarriage in clinically recognized pregnancies in the U.S. general population is 15% to 20%.

In animal reproduction studies, no evidence of major adverse developmental outcomes was observed following oral administration of fosamprenavir. Systemic exposure to amprenavir (the active ingredient) was less than (rabbits) or up to 2 times (rats) those in humans at the maximum recommended human dose (MRHD) with or without ritonavir. In contrast, oral administration of amprenavir was associated with abortions in pregnant rabbits at doses that produced approximately one-twentieth the human exposure at the MRHD.

In the rat pre- and postnatal development study, toxicities to the offspring, including reduced survival and reproductive performance, were observed at maternal systemic exposures (AUC) to amprenavir that were approximately 2 times the exposure in humans at the MRHD of fosamprenavir alone or approximately the same as those seen in humans following administration of the MRHD of fosamprenavir in combination with ritonavir (see Data).

Clinical Considerations

Virologic Monitoring During Pregnancy and the Postpartum Period:Based on limited data on the use of fosamprenavir calcium during pregnancy, no dosage adjustments are required for pregnant patients who are already on a stable twice-daily regimen of fosamprenavir calcium 700 mg taken with ritonavir 100 mg prior to pregnancy, and who are virologically suppressed (HIV-1 RNA less than 50 copies per mL) [see Dosage and Administration (2.3), Clinical Pharmacology (12.3)]. In a clinical trial of 10 HIV-1–infected pregnant women treated with fosamprenavir calcium 700 mg taken with ritonavir 100 mg twice daily through postpartum, total amprenavir exposures were lower during pregnancy compared with the postpartum period. Therefore, viral load should be monitored closely to ensure viral suppression is maintained [see Data, Dosage and Administration (2.2), Clinical Pharmacology (12.3)]. Pregnancy data with other dosage regimens of fosamprenavir calcium (with or without ritonavir) are not available.

Data

Human Data:fosamprenavir calcium 700 mg taken with ritonavir 100 mg twice daily in combination with a background regimen was evaluated in a clinical trial of 10 HIV-1–infected pregnant women during the second and third trimesters and postpartum. Subjects initiated fosamprenavir calcium /ritonavir during pregnancy at a median of 19 weeks’ gestation; 4 had undetectable HIV-1 RNA viral load (less than 50 copies/mL) at the time of initiation. Amprenavir pharmacokinetics and placental transfer were studied during the second trimester (n = 6) or third trimester (n = 9) and postpartum (n = 9). Pregnancy outcomes were available for all 10 subjects, among which 1 twin pregnancy was included. Compared to the postpartum period, geometric mean amprenavir AUC was 35% lower in the second trimester and 25% lower in the third trimester. The amprenavir geometric mean ratio (95% CI) of fetal cord to maternal peripheral plasma concentration (n = 7) was 0.27 (0.24 to 0.30) [see Clinical Pharmacology (12.3)].At delivery, 9 subjects had HIV-1 viral load less than 50 copies/mL, and 1 subject had a viral load of 111 copies/mL. All 11 infants born had test results that were negative for HIV-1 at the time of delivery and through 12 months postpartum. There were no new safety findings compared with the known safety profile of fosamprenavir calcium /ritonavir in HIV-1–infected adults.

Based on prospective reports to the APR of approximately 146 live births following exposure to fosamprenavir-containing regimens, there were 2 birth defects reported in 109 first trimester exposures and 2 birth defects reported in 36 second and third trimester exposures. The background rate for major birth defects is 2.7% in a U.S. reference population of the MACDP. Prospective reports from the APR of overall major birth defects in pregnancies exposed to fosamprenavir are compared with the U.S. background major birth defect rate. Methodological limitations of the APR include the use of MACDP as the external comparator group. Limitations of using an external comparator include differences in methodology and populations as well as confounding due to the underlying disease.

Animal Data:Fosamprenavir was administered orally to pregnant rats (300, 820, or 2,240 mg per kg per day) and rabbits (74.8, 224.3, or 672.8 mg per kg per day) on Gestation Days 6 to 17 and Days 7 to 20, respectively. No major adverse effects on embryo-fetal development were observed at these dose levels, resulting in exposures (AUC0-24 h) approximately 2 times (rats) and 0.8 times (rabbits) human exposures at the MRHD of fosamprenavir alone or 0.7 times (rats) and 0.3 times (rabbits) human exposures at the MRHD of fosamprenavir in combination with ritonavir. However, increased incidence of abortion was observed in rabbits administered a maternally toxic dose of fosamprenavir (672.8 mg per kg per day). In a study where amprenavir was administered orally to pregnant rabbits (25, 50, or 100 mg per kg per day) on Gestation Days 8 to 20, increased abortions and an increased incidence of minor skeletal variations (deficient ossification of the femur, humerus, and trochlea) were observed at doses that produced approximately one-twentieth the exposure seen at the MRHD.

In the rat pre- and postnatal development study, fosamprenavir was administered orally (300, 820, or 2,240 mg per kg per day) on Gestation Day 6 to Lactation/Postpartum Day 20. Fosamprenavir caused a reduction in pup survival and body weights. In surviving female offspring from the high-dose group, an increased time to successful mating, an increased length of gestation, a reduced number of uterine implantation sites per litter, and reduced gestational body weights were observed. Systemic exposure (AUC0-24 h) to amprenavir in rats was approximately 2 times the exposures in humans at the MRHD of fosamprenavir alone or approximately the same as those seen in humans at the MRHD of fosamprenavir in combination with ritonavir.

8.2 Lactation

Risk Summary

The Centers for Disease Control and Prevention recommends that HIV-1-infected mothers in the United States not breastfeed their infants to avoid risking postnatal transmission of HIV-1 infection.

There is no information available on the presence of amprenavir in human milk, the effects of the drug on the breastfed infant, or the effects of the drug on milk production. When administered to lactating rats, amprenavir was present in milk (see Data). Because of the potential for (1) HIV-1 transmission (in HIV-negative infants), (2) developing viral resistance (in HIV-positive infants), and (3) adverse reactions in a breastfed infant, instruct mothers not to breastfeed if they are receiving fosamprenavir calcium.

Data

Amprenavir was excreted into the milk of lactating rats following a single dose of amprenavir (100 mg per kg); a maximal milk concentration was achieved 2 hours post-administration at a milk concentration approximately 1.2 times that of maternal plasma concentrations.

8.3 Females and Males of Reproductive Potential

Contraception

Use of fosamprenavir calcium may reduce the efficacy of combined hormonal contraceptives. Advise patients using combined hormonal contraceptives to use an effective alternative contraceptive method or an additional barrier method of contraception [see Drug Interactions (7.2)].

8.4 Pediatric Use

The safety, pharmacokinetic profile, and virologic and immunologic responses of fosamprenavir calcium with and without ritonavir were evaluated in protease inhibitor-naive and -experienced HIV-1–infected pediatric subjects aged at least 4 weeks to younger than 18 years and weighing at least 3 kg in 3 open-label trials [see Adverse Reactions (6.1), Clinical Pharmacology (12.3), Clinical Studies (14.3)].

Treatment with fosamprenavir calcium is not recommended in protease inhibitor-experienced pediatric patients younger than 6 months. The pharmacokinetics, safety, tolerability, and efficacy of fosamprenavir calcium in pediatric patients younger than 4 weeks have not been established [see Clinical Pharmacology (12.3)]. Available pharmacokinetic and clinical data do not support once-daily dosing of fosamprenavir calcium alone or in combination with ritonavir for any pediatrics or twice-daily dosing without ritonavir in pediatric patients younger than 2 years [see Clinical Pharmacology (12.3), Clinical Studies (14.3)]. See Dosage and Administration (2.3)for dosing recommendations for pediatric patients.

8.5 Geriatric Use

Clinical studies of fosamprenavir calcium did not include sufficient numbers of patients aged 65 and over to determine whether they respond differently from younger adults. In general, dose selection for an elderly patient should be cautious, reflecting the greater frequency of decreased hepatic, renal, or cardiac function and of concomitant disease or other drug therapy.

8.6 Hepatic Impairment

Amprenavir is principally metabolized by the liver; therefore, caution should be exercised when administering fosamprenavir calcium to patients with hepatic impairment because amprenavir concentrations may be increased [see Clinical Pharmacology (12.3)]. Patients with impaired hepatic function receiving fosamprenavir calcium with or without concurrent ritonavir require dose reduction [see Dosage and Administration (2.4)].

There are no data to support dosing recommendations for pediatric subjects with hepatic impairment.

10 OVERDOSAGE

In a healthy volunteer repeat-dose pharmacokinetic trial evaluating high-dose combinations of fosamprenavir calcium plus ritonavir, an increased frequency of Grade 2/3 ALT elevations (greater than 2.5 x ULN) was observed with fosamprenavir calcium 1,400 mg twice daily plus ritonavir 200 mg twice daily (4 of 25 subjects). Concurrent Grade 1/2 elevations in AST (greater than 1.25 x ULN) were noted in 3 of these 4 subjects. These transaminase elevations resolved following discontinuation of dosing.

There is no known antidote for fosamprenavir calcium. It is not known whether amprenavir can be removed by peritoneal dialysis or hemodialysis, although it is unlikely as amprenavir is highly protein bound. If overdosage occurs, the patient should be monitored for evidence of toxicity and standard supportive treatment applied as necessary.

11 DESCRIPTION

Fosamprenavir calcium, USP is a prodrug of amprenavir, an inhibitor of HIV protease. The chemical name of fosamprenavir calcium, USP is (3S)-tetrahydrofuran-3-yl (1S,2R)-3-[[(4-aminophenyl) sulfonyl](isobutyl)amino]-1-benzyl-2-(phosphonooxy) propylcarbamate monocalcium salt. Fosamprenavir calcium, USP is a single stereoisomer with the (3S)(1S,2R) configuration. It has a molecular formula of C25H34CaN3O9PS and a molecular weight of 623.7. It has the following structural formula:

Fosamprenavir calcium, USP is a white to cream color solid which is soluble in methanol.

Fosamprenavir calcium tablets, USP are available for oral administration in a strength of 700 mg of fosamprenavir as fosamprenavir calcium, USP (equivalent to approximately 600 mg of amprenavir). Each 700 mg tablet contains the inactive ingredients colloidal silicon dioxide, croscarmellose sodium, magnesium stearate, microcrystalline cellulose, and povidone. The tablet coating contains the inactive ingredients ethylcellulose, ferric oxide red, hypromellose, talc, and titanium dioxide. The imprinting ink contains the inactive ingredients ferric oxide black, propylene glycol, and shellac.

FDA approved dissolution test specifications differ from USP.

12 CLINICAL PHARMACOLOGY

12.1 Mechanism of Action

Fosamprenavir is an HIV-1 antiretroviral agent [see Microbiology (12.4)].

12.3 Pharmacokinetics

The pharmacokinetic properties of amprenavir after administration of fosamprenavir calcium, with or without ritonavir, have been evaluated in both healthy adult volunteers and in HIV-1-infected subjects; no substantial differences in steady-state amprenavir concentrations were observed between the 2 populations.

The pharmacokinetic parameters of amprenavir after administration of fosamprenavir calcium (with and without concomitant ritonavir) are shown in Table 7.

Table 7. Geometric Mean (95% CI) Steady-State Plasma Amprenavir Pharmacokinetic Parameters in Adults

Regimen | Cmax; (mcg/mL) | Tmax; (hours)a | AUC24; (mcg•h/mL) | Ctaub; (mcg/mL)
Fosamprenavir calcium 1,400 mg Twice Daily(n = 22)c | 4.82; (4.06 to 5.72) | 1.3; (0.8to 4) | 33d; (27.6to 39.2) | 0.35; (0.27to 0.46)
Fosamprenavir calcium 1,400 mg Once Daily plus Ritonavir 200 mg Once Daily (n = 22)e | 7.24; (6.32 to 8.28) | 2.1; (0.8t o 5) | 69.4; (59.7 to 80.8) | 1.45; (1.16 to 1.81)
Fosamprenavir calcium 1,400 mg Once Daily plus Ritonavir 100 mg Once Daily (n = 36)e | 7.93; (7.25 to 8.68) | 1.5; (0.75 to 5) | 66.4; (61.1 to 72.1) | 0.86; (0.74 to 1.01)
Fosamprenavir calcium 700 mg Twice Daily plus Ritonavir 100 mg Twice Daily (n = 24)e | 6.08; (5.38 to 6.86) | 1.5; (0.75 to 5) | 79.2d; (69 to 90.6) | 2.12; (1.77 to 2.54)

aData shown are median (range).

bCtauis the concentration at the end of the dose interval.

cHIV-infected adults.

dAUC24was calculated from AUC12summary data x 2.

eHealthy adults.

The mean plasma amprenavir concentrations of the dosing regimens over the dosing intervals are displayed in Figure 1.

Figure 1. Mean (±SD) Steady-State Plasma Amprenavir Concentrations and Mean EC50Values against HIV from Protease Inhibitor-Naive Subjects (in the Absence of Human Serum)

Absorption

After administration of a single dose of fosamprenavir calcium to HIV-1-infected subjects, the time to peak amprenavir concentration (Tmax) occurred between 1.5 and 4 hours (median 2.5 hours). The absolute oral bioavailability of amprenavir after administration of fosamprenavir calcium in humans has not been established.

After administration of a single 1,400-mg dose in the fasted state, fosamprenavir calcium oral suspension (50 mg per mL) and fosamprenavir calcium tablets (700 mg) provided similar amprenavir exposures (AUC); however, the Cmaxof amprenavir after administration of the suspension formulation was 14.5% higher compared with the tablet.

Amprenavir is both a substrate for and inducer of P-glycoprotein.

Effects of Food on Oral Absorption

Administration of a single 1,400 mg dose of fosamprenavir calcium tablets in the fed state (standardized high-fat meal: 967 kcal, 67 grams fat, 33 grams protein, 58 grams carbohydrate) compared with the fasted state was associated with no significant changes in amprenavir Cmax, Tmax, or AUC0-∞[see Dosage and Administration (2)].

Administration of a single 1,400 mg dose of fosamprenavir calcium oral suspension in the fed state (standardized high-fat meal: 967 kcal, 67 grams fat, 33 grams protein, 58 grams carbohydrate) compared with the fasted state was associated with a 46% reduction in Cmax, a 0.72-hour delay in Tmax, and a 28% reduction in amprenavir AUC0-∞.

Distribution

In vitro, amprenavir is approximately 90% bound to plasma proteins, primarily to alpha1-acid glycoprotein. In vitro, concentration-dependent binding was observed over the concentration range of 1 to 10 mcg per mL, with decreased binding at higher concentrations. The partitioning of amprenavir into erythrocytes is low, but increases as amprenavir concentrations increase, reflecting the higher amount of unbound drug at higher concentrations.

Metabolism

After oral administration, fosamprenavir is rapidly and almost completely hydrolyzed to amprenavir and inorganic phosphate prior to reaching the systemic circulation. This occurs in the gut epithelium during absorption. Amprenavir is metabolized in the liver by the CYP3A4 enzyme system. The 2 major metabolites result from oxidation of the tetrahydrofuran and aniline moieties. Glucuronide conjugates of oxidized metabolites have been identified as minor metabolites in urine and feces.

Elimination

Excretion of unchanged amprenavir in urine and feces is minimal. Unchanged amprenavir in urine accounts for approximately 1% of the dose; unchanged amprenavir was not detectable in feces. Approximately 14% and 75% of an administered single dose of^14C-amprenavir can be accounted for as metabolites in urine and feces, respectively. Two metabolites accounted for greater than 90% of the radiocarbon in fecal samples. The plasma elimination half-life of amprenavir is approximately 7.7 hours.

Specific Populations

Patients with Hepatic Impairment: The pharmacokinetics of amprenavir have been studied after the administration of fosamprenavir calcium in combination with ritonavir to adult HIV-1-infected subjects with mild, moderate, and severe hepatic impairment. Following 2 weeks of dosing with fosamprenavir calcium plus ritonavir, the AUC of amprenavir was increased by approximately 22% in subjects with mild hepatic impairment, by approximately 70% in subjects with moderate hepatic impairment, and by approximately 80% in subjects with severe hepatic impairment compared with HIV-1-infected subjects with normal hepatic function. Protein binding of amprenavir was decreased in subjects with hepatic impairment. The unbound fraction at 2 hours (approximate Cmax) ranged between a decrease of -7% to an increase of 57% while the unbound fraction at the end of the dosing interval (Cmin) increased from 50% to 102% [see Dosage and Administration (2.4)].

The pharmacokinetics of amprenavir have been studied after administration of amprenavir given as Agenerase®capsules to adult subjects with hepatic impairment. Following administration of a single 600-mg oral dose, the AUC of amprenavir was increased by approximately 2.5-fold in subjects with moderate cirrhosis and by approximately 4.5-fold in subjects with severe cirrhosis compared with healthy volunteers [see Dosage and Administration (2.4)].

Patients with Renal Impairment:The impact of renal impairment on amprenavir elimination in adults has not been studied. The renal elimination of unchanged amprenavir represents approximately 1% of the administered dose; therefore, renal impairment is not expected to significantly impact the elimination of amprenavir.

Pregnant Women:Amprenavir pharmacokinetics were studied in pregnant women receiving fosamprenavir calcium (700 mg) plus ritonavir (100 mg) twice daily during the second trimester (n = 6) or third trimester (n = 9) and postpartum (n = 9). Compared to postpartum, geometric mean amprenavir AUC was 35% lower in the second trimester and 25% lower in the third trimester (Table 8). This decrease results in amprenavir concentrations that are within the range observed across regimens of fosamprenavir calcium in non-pregnant adults and lower concentrations compared with fosamprenavir calcium (700 mg) plus ritonavir (100 mg) twice daily in non-pregnant adults (Table 7, Table 8). This decrease is not expected to be considered clinically relevant in patients who are virologically suppressed; however, viral load should be monitored closely to ensure viral suppression is maintained [see Dosage and Administration (2.2), Use in Specific Populations (8.1)]. The amprenavir geometric mean ratio (95% CI) of fetal cord to maternal peripheral plasma concentration (n = 7) was 0.27 (0.24 to 0.30).

Table 8. Geometric Mean (95% CI) Steady-State Plasma Amprenavir Pharmacokinetic Parameters in Pregnant Women Receiving Fosamprenavir calcium with Ritonavir

Pharmacokinetic Parameter | Fosamprenavir calcium 700 mg Twice Daily plus Ritonavir 100 mg Twice Daily
Pharmacokinetic Parameter | Second Trimester; (n = 6) | Third Trimester; (n = 9) | Postpartum; (n = 9)
AUC12(mcg•h/mL) | 26.0; (19.5, 34.6) | 30.1; (21.6, 41.9) | 39.9; (31.9, 50.1)
AUC24(mcg•h/mL)a | 52.0; (39.0, 69.2) | 60.2; (43.2, 83.8) | 79.8; (63.8, 100.2)
Cmax(mcg/mL) | 4.19; (3.19, 5.51) | 5.36; (3.98, 7.22) | 6.65; (5.24, 8.44)
Ctau(mcg/mL)b | 1.31; (0.97, 1.77) | 1.34; (0.95, 1.89) | 2.03; (1.46, 2.83)

aAUC24was calculated from AUC12summary data x 2.

bCtaurepresents the concentration at the end of the dose interval.

Pediatric Patients:The pharmacokinetics of amprenavir following administration of fosamprenavir calcium oral suspension and fosamprenavir calcium tablets, with or without ritonavir, have been studied in a total of 212 HIV-1-infected pediatric subjects enrolled in 3 trials. Fosamprenavir calcium without ritonavir was administered as 30 or 40 mg per kg twice daily to children aged 2 to 5 years. Fosamprenavir calcium with ritonavir was administered as fosamprenavir calcium 30 mg per kg plus ritonavir 6 mg per kg once daily to children aged 2 to 18 years and as fosamprenavir calcium 18 to 60 mg per kg plus ritonavir 3 to 10 mg per kg twice daily to children aged at least 4 weeks to 18 years; body weights ranged from 3 to 103 kg.

Amprenavir apparent clearance decreased with increasing weight. Weight-adjusted apparent clearance was higher in children younger than 4 years, suggesting that younger children require higher mg-per-kg dosing of fosamprenavir calcium.

The pharmacokinetics of fosamprenavir calcium oral suspension in protease inhibitor-naive infants younger than 6 months (n = 9) receiving fosamprenavir calcium 45 mg per kg plus ritonavir 10 mg per kg twice daily generally demonstrated lower AUC12and Cminthan adults receiving twice-daily fosamprenavir calcium 700 mg plus ritonavir 100 mg, the dose recommended for protease-experienced adults. The mean steady-state amprenavir AUC12, Cmax, and Cminwere 26.6 mcg•hour per mL, 6.25 mcg per mL, and 0.86 mcg per mL, respectively. Because of expected low amprenavir exposure and a requirement for large volume of drug, twice-daily dosing of fosamprenavir calcium alone (without ritonavir) in pediatric subjects younger than 2 years was not studied.

Pharmacokinetic parameters for fosamprenavir calcium administered with food and with ritonavir in this patient population at the recommended weight-band–based dosage regimens are provided in Table 9.

Table 9. Geometric Mean (95% CI) Steady-State Plasma Amprenavir Pharmacokinetic Parameters by Weight in Pediatric and Adolescent Subjects Aged at Least 4 Weeks to 18 Years Receiving Fosamprenavir Calcium with Ritonavir

Weight | Recommended Dosage Regimen | Cmax |  | AUC24 |  | Cmin
 |  | n | (mcg/mL) | n | (mcg•h/mL) | n | (mcg/mL)
< 11 kg | Fosamprenavir calcium 45 mg/kg plus Ritonavir 7 mg/kg twice daily | 12 | 6 (3.88, 9.29) | 12 | 57.3; (34.1, 96.2) | 27 | 1.65; (1.22, 2.24)
11 kg - < 15 kg | Fosamprenavir calcium 30 mg/kg plus Ritonavir 3 mg/kg twice daily | Not studieda
15 kg - < 20 kg | Fosamprenavir calcium 23 mg/kg plus Ritonavir 3 mg/kg twice daily | 5 | 9.54; (4.63, 19.7) | 5 | 121; (54.2, 269) | 9 | 3.56; (2.33, 5.43)
20 kg - < 39 kg | Fosamprenavir calcium 18 mg/kg plus Ritonavir 3 mg/kg twice daily | 13 | 6.24; (5.01, 7.77) | 12 | 97.9; (77, 124) | 23 | 2.54; (2.11, 3.06)
≥ 39 kg | Fosamprenavir calcium 700 mg plus Ritonavir 100 mg twice daily | 15 | 5.03; (4.04, 6.26) | 15 | 72.3; (59.6, 87.6) | 42 | 1.98; (1.72, 2.29)

aRecommended dose for pediatric patients weighing 11 kg to less than 15 kg is based on population pharmacokinetic analysis.

Subjects aged 2 to younger than 6 years receiving fosamprenavir calcium 30 mg per kg twice daily without ritonavir achieved geometric mean (95% CI) amprenavir Cmax(n = 9), AUC12(n = 9), and Cmin(n = 19) of 7.15 (5.05, 10.1), 22.3 (15.3, 32.6), and 0.513 (0.384, 0.686), respectively.

Geriatric Patients:The pharmacokinetics of amprenavir after administration of fosamprenavir calcium to patients older than 65 years have not been studied [see Use in Specific Populations(8.5)].

Male and Female Patients:The pharmacokinetics of amprenavir after administration of fosamprenavir calcium do not differ between males and females.

Racial Groups:The pharmacokinetics of amprenavir after administration of fosamprenavir calcium do not differ between blacks and non-blacks.

Drug Interaction Studies

[See Contraindications (4), Warnings and Precautions (5.1), Drug Interactions (7). ]

Amprenavir, the active metabolite of fosamprenavir, is metabolized in the liver by the cytochrome P450 enzyme system. Amprenavir inhibits CYP3A4. Data also suggest that amprenavir induces CYP3A4. Caution should be used when coadministering medications that are substrates, inhibitors, or inducers of CYP3A4, or potentially toxic medications that are metabolized by CYP3A4. Amprenavir does not inhibit CYP2D6, CYP1A2, CYP2C9, CYP2C19, CYP2E1, or uridine glucuronosyltransferase (UDPGT). Amprenavir is both a substrate for and inducer of P-glycoprotein.

Drug interaction trials were performed with fosamprenavir calcium and other drugs likely to be coadministered or drugs commonly used as probes for pharmacokinetic interactions. The effects of coadministration on AUC, Cmax, and Cminvalues are summarized in Table 10 (effect of other drugs on amprenavir) and Table 12 (effect of fosamprenavir calcium on other drugs). In addition, since fosamprenavir calcium delivers comparable amprenavir plasma concentrations as Agenerase, drug interaction data derived from trials with Agenerase are provided in Tables 11 and 13. For information regarding clinical recommendations, [see Drug Interactions (7)].

Table 10. Drug Interactions: Pharmacokinetic Parameters for Amprenavir after Administration of Fosamprenavir Calcium in the Presence of the Coadministered Drug(s)

Coadministered Drug(s) and Dose(s) | Dose of Fosamprenavir Calciuma | n | % Change in Amprenavir Pharmacokinetic Parameters (90% CI)
Coadministered Drug(s) and Dose(s) | Dose of Fosamprenavir Calciuma | n | Cmax | AUC | Cmin
Antacid (MAALOX TC); 30 mL single dose | 1,400-mg; single dose | 30 | ↓ 35; (↓ 24 to ↓ 42) | ↓ 18; (↓ 9 to ↓ 26) | ↑ 14; (↓ 7 to ↑ 39)
Atazanavir; 300 mg once daily for 10 days | 700 mg twice daily plus ritonavir 100 mg twice daily for 10 days | 22 | ↔ | ↔ | ↔
Atorvastatin; 10 mg once daily for 4 days | 1,400 mg twice daily for 2 weeks | 16 | ↓ 18; (↓ 34 to ↑ 1) | ↓ 27; (↓ 41 to ↓ 12) | ↓ 12; (↓ 27 to ↓ 6)
Atorvastatin; 10 mg once daily for 4 days | 700 mg twice daily plus ritonavir 100 mg twice daily for 2 weeks | 16 | ↔ | ↔ | ↔
Efavirenz; 600 mg once daily for 2 weeks | 1,400 mg once daily plus ritonavir 200 mg once daily for 2 weeks | 16 | ↔ | ↓ 13; (↓ 30 to ↑ 7) | ↓ 36; (↓ 8 to ↓ 56)
Efavirenz; 600 mg once daily plus additional ritonavir 100 mg once daily for 2 weeks | 1,400 mg once daily plus ritonavir 200 mg once daily for 2 weeks | 16 | ↑ 18; (↑ 1 to ↑ 38) | ↑ 11; (0 to ↑ 24) | ↔
Efavirenz; 600 mg once daily for 2 weeks | 700 mg twice daily plus ritonavir 100 mg twice daily for 2 weeks | 16 | ↔ | ↔ | ↓ 17; (↓ 4 to ↓ 29)
Esomeprazole; 20 mg once daily for 2 weeks | 1,400 mg twice daily for 2 weeks | 25 | ↔ | ↔ | ↔
Esomeprazole; 20 mg once daily for 2 weeks | 700 mg twice daily plus ritonavir 100 mg twice daily for 2 weeks | 23 | ↔ | ↔ | ↔
Ethinyl estradiol/norethindrone; 0.035 mg/0.5 mg once daily for 21 days | 700 mg twice daily plus ritonavirb100 mg twice daily for 21 days | 25 | ↔c | ↔c | ↔c
Ketoconazoled; 200 mg once daily for 4 days | 700 mg twice daily plus ritonavir 100 mg twice daily for 4 days | 15 | ↔ | ↔ | ↔
Lopinavir/ritonavir; 533 mg/133 mg twice daily | 1,400 mg twice daily for 2 weeks | 18 | ↓ 13e | ↓ 26e | ↓ 42e
Lopinavir/ritonavir; 400 mg/100 mg twice daily for 2 weeks | 700 mg twice daily plus ritonavir 100 mg twice daily for 2 weeks | 18 | ↓ 58; (↓ 42 to ↓ 70) | ↓ 63; (↓ 51 to ↓ 72) | ↓ 65; (↓ 54 to ↓ 73)
Maraviroc; 300 mg twice daily for 10 days | 700 mg twice daily plus ritonavir; 100 mg twice daily for; 20 days | 14 | ↓ 34; (↓ 25 to ↓41) | ↓ 35; (↓ 29 to ↓ 41) | ↓ 36; (↓ 27 to ↓ 43)
Maraviroc; 300 mg once daily for 10 days | 1,400 mg once daily; plus ritonavir; 100 mg once daily for; 20 days | 14 | ↓ 29; (↓ 20 to ↓38) | ↓30; (↓23 to ↓36) | ↓ 15; (↓3 to ↓25)
Methadone; 70 to 120 mg once daily for 2 weeks | 700 mg twice daily plus ritonavir 100 mg twice daily for 2 weeks | 19 | ↔c | ↔c | ↔c
Nevirapine; 200 mg twice daily for 2 weeksf | 1,400 mg twice daily for 2 weeks | 17 | ↓ 25; (↓ 37 to ↓ 10) | ↓ 33; (↓ 45 to ↓ 20) | ↓ 35; (↓ 50 to ↓ 15)
Nevirapine; 200 mg twice daily. for 2 weeksf | 700 mg twice daily plus ritonavir 100 mg twice daily for 2 weeks | 17 | ↔ | ↓ 11; (↓ 23 to ↑ 3) | ↓ 19; (↓ 32 to ↓ 4)
Phenytoin; 300 mg once daily for 10 days | 700 mg twice daily plus ritonavir 100 mg twice daily for 10 days | 13 | ↔ | ↑ 20; (↑ 8 to ↑ 34) | ↑ 19; (↑ 6 to ↑ 33)
Raltegravir; 400 mg twice daily for 14 days | 1,400 mg twice daily for 14 days (fasted) | 14 | ↓ 27; (↓ 46 to ↔) | ↓ 36; (↓ 53 to ↓ 13) | ↓ 43g; (↓ 59 to ↓ 21)
Raltegravir; 400 mg twice daily for 14 days | 1,400 mg twice daily for 14 daysh | 14 | ↓ 15; (↓ 27 to ↓ 1) | ↓ 17; (↓ 27 to ↓ 6) | ↓ 32g; (↓ 53 to ↓ 1)
Raltegravir; 400 mg twice daily for 14 days | 700 mg twice daily plus ritonavir 100 mg twice daily for 14 days (fasted) | 14 | ↓ 14; (↓ 39 to ↑ 20) | ↓ 17; (↓ 38 to ↑ 12) | ↓ 20g; (↓ 45 to ↑ 17)
Raltegravir; 400 mg twice daily for 14 days | 700 mg twice daily plus ritonavir 100 mg twice daily for 14 days | 12 | ↓ 25; (↓ 42 to ↓ 2) | ↓ 25; (↓ 44 to ↔) | ↓ 33g; (↓ 52 to ↓ 7)
Raltegravir; 400 mg twice daily. for 14 days | 1,400 mg once daily plus ritonavir 100 mg once daily for 14 days (fasted) | 13 | ↓ 18; (↓ 34 to ↔) | ↓ 24; (↓ 41 to ↔) | ↓ 50g; (↓ 64 to ↓ 31)
Raltegravir; 400 mg twice daily. for 14 days | 1,400 mg once daily plus ritonavir 100 mg once daily for 14 daysh | 14 | ↑ 27; (↓ 1 to ↑ 62) | ↑ 13; (↓ 7 to ↑ 38) | ↓ 17g; (↓ 45 to ↑ 26)
Ranitidine; 300 mg single dose (administered 1 hour before fosamprenavir) | 1,400 mg single dose | 30 | ↓ 51; (↓ 43 to ↓ 58) | ↓ 30; (↓ 22 to ↓ 37) | ↔; (↓ 19 to ↑ 21)
Rifabutin; 150 mg every other day for 2 weeks | 700 mg twice daily plus ritonavir 100 mg twice daily for 2 weeks | 15 | ↑ 36c; (↑ 18 to ↑ 55) | ↑ 35c; (↑ 17 to ↑ 56) | ↑ 17c; (↓ 1 to ↑ 39)
Tenofovir; 300 mg once daily for 4 to 48 weeks | 700 mg twice daily plus ritonavir 100 mg twice daily for 4 to 48 weeks | 45 | NA | NA | ↔i
Tenofovir; 300 mg once daily for 4 to 48 weeks | 1,400 mg once daily plus ritonavir 200 mg once daily for 4 to 48 weeks | 60 | NA | NA | ↔i

aConcomitant medication is also shown in this column where appropriate.

bRitonavir Cmax, AUC, and Cminincreased by 63%, 45%, and 13%, respectively, compared with historical control.

cCompared with historical control.

dSubjects were receiving fosamprenavir calcium/ritonavir for 10 days prior to the 4-day treatment period with both ketoconazole and fosamprenavir calcium/ritonavir.

eCompared with fosamprenavir calcium 700 mg/ritonavir 100 mg twice daily for 2 weeks.

fSubjects were receiving nevirapine for at least 12 weeks prior to trial.

gClast(C12 hor C24 h).

hDoses of fosamprenavir calcium and raltegravir were given with food on pharmacokinetic sampling days and without regard to food all other days.

iN = 18 for Cmin.

jCompared with parallel control group.

↑ = Increase; ↓ = Decrease; ↔ = No change (↑ or ↓ less than or equal to 10%), NA = Not applicable.

Table 11. Drug Interactions: Pharmacokinetic Parameters for Amprenavir after Administration of Agenerase in the Presence of the Coadministered Drug(s)

Coadministered Drug(s) and Dose(s) | Dose of; Agenerasea | n | % Change in Amprenavir Pharmacokinetic Parameters; (90% CI)
Coadministered Drug(s) and Dose(s) | Dose of; Agenerasea | n | Cmax | AUC | Cmin
Abacavir; 300 mg twice daily for 2 to 3 weeks | 900 mg twice daily; for 2 to 3 weeks | 4 | ↔a | ↔a | ↔a
Clarithromycin; 500 mg twice daily for 4 days | 1,200 mg twice daily; for 4 days | 12 | ↑ 15; (↑ 1 to ↑ 31) | ↑ 18; (↑ 8 to ↑ 29) | ↑ 39; (↑ 31 to ↑ 47)
Delavirdine; 600 mg twice daily for 10 days | 600 mg twice daily; for 10 days | 9 | ↑ 40b | ↑ 130b | ↑ 125b
Ethinyl estradiol/norethindrone; 0.035 mg/1 mg for 1 cycle | 1,200 mg twice daily; for 28 days | 10 | ↔ | ↓ 22; (↓ 35 to ↓ 8) | ↓ 20; (↓ 41 to ↑ 8)
Indinavir; 800 mg 3 times a day for 2 weeks (fasted) | 750 or 800 mg 3 times a day for 2 weeks (fasted) | 9 | ↑ 18; (↑ 13 to ↑ 58) | ↑ 33; (↑ 2 to ↑ 73) | ↑ 25; (↓ 27 to ↑ 116)
Ketoconazole; 400-mg single dose | 1,200-mg; single dose | 12 | ↓ 16; (↓ 25 to ↓ 6) | ↑ 31; (↑ 20 to ↑ 42) | NA
Lamivudine; 150-mg single dose | 600-mg; single dose | 11 | ↔ | ↔ | NA
Methadone; 44 to 100 mg once daily for; > 30 days | 1,200 mg mg twice daily; for 10 days | 16 | ↓ 27c | ↓ 30c | ↓ 25c
Nelfinavir; 750 mg 3 times a day for 2 weeks (fed) | 750 or 800 mg 3 times a day for 2 weeks (fed) | 6 | ↓ 14; (↓ 38 to ↑ 20) | ↔ | ↑ 189; (↑ 52 to ↑ 448)
Rifabutin; 300 mg once daily for 10 days | 1,200 mg twice daily; for 10 days | 5 | ↔ | ↓ 15; (↓ 28 to 0) | ↓ 15; (↓ 38 to ↑ 17)
Rifampin; 300 mg once daily for 4 days | 1,200 mg twice daily; for 4 days | 11 | ↓ 70; (↓ 76 to ↓ 62) | ↓ 82; (↓ 84 to ↓ 78) | ↓ 92; (↓ 95 to ↓ 89)
Saquinavir; 800 mg 3 times a day for 2 weeks (fed) | 750 or 800 mg 3 times a day for 2 weeks (fed) | 7 | ↓ 37; (↓ 54 to ↓ 14) | ↓ 32; (↓ 49 to ↓ 9) | ↓ 14; (↓ 52 to ↑ 54)
Zidovudine; 300-mg single dose | 600-mg; single dose | 12 | ↔ | ↑ 13; (↓ 2 to ↑ 31) | NA

aCompared with parallel control group.

bMedian percent change; confidence interval not reported.

cCompared with historical data.

↑ = Increase; ↓ = Decrease; ↔ = No change (↑ or ↓ less than 10%); NA = Cminnot calculated for single-dose trial.

Table 12. Drug Interactions: Pharmacokinetic Parameters for Coadministered Drug in the Presence of Amprenavir after Administration of Fosamprenavir Calcium

Coadministered Drug(s) and Dose(s) | Dose of Fosamprenavir Calciuma | n | % Change in Pharmacokinetic Parameters of Coadministered Drug (90% CI)
Coadministered Drug(s) and Dose(s) | Dose of Fosamprenavir Calciuma | n | Cmax | AUC | Cmin
Atazanavir; 300 mg once daily for 10 daysb | 700 mg twice daily plus ritonavir 100 mg twice daily for 10 days | 21 | ↓ 24; (↓ 39 to ↓ 6) | ↓ 22; (↓ 34 to ↓ 9) | ↔
Atorvastatin; 10 mg once daily for 4 days | 1,400 mg twice daily for 2 weeks | 16 | ↑ 304; (↑ 205 to ↑ 437) | ↑ 130; (↑ 100 to ↑ 164) | ↓ 10; (↓ 27 to ↑ 12)
Atorvastatin; 10 mg once daily for 4 days | 700 mg twice daily plus ritonavir 100 mg twice daily for 2 weeks | 16 | ↑ 184; (↑ 126 to ↑ 257) | ↑ 153; (↑ 115 to ↑ 199) | ↑ 73; (↑ 45 to ↑ 108)
Esomeprazole; 20 mg once daily for 2 weeks | 1,400 mg twice daily for 2 weeks | 25 | ↔ | ↑ 55; (↑ 39 to ↑ 73) | ND
Esomeprazole; 20 mg once daily for 2 weeks | 700 mg twice daily plus ritonavir 100 mg twice daily for 2 weeks | 23 | ↔ | ↔ | ND
Ethinyl estradiolc; 0.035 mg once daily for 21 days | 700 mg twice daily plus ritonavir 100 mg twice daily for 21 days | 25 | ↓ 28; (↓ 21 to ↓ 35) | ↓ 37; (↓ 30 to ↓ 42) | ND
Dolutegravir 50 mg once daily | 700 mg twice daily plus ritonavir 100 mg twice daily | 12 | ↓24 (↓8 to ↓37) | ↓35 (↓22 to ↓46) | ↓49 (↓37 to ↓59)
Ketoconazoled; 200 mg once daily for 4 days | 700 mg twice daily plus ritonavir 100 mg twice dailyfor 4 days | 15 | ↑ 25; (↑ 0 to ↑ 56) | ↑ 169; (↑ 108 to ↑ 248) | ND
Lopinavir/ritonavire; 533 mg/133 mg twice daily for 2 weeks | 1,400 mg twice daily for 2 weeks | 18 | ↔f | ↔f | ↔f
Lopinavir/ritonavire; 400 mg/100 mg twice daily for 2 weeks | 700 mg twice daily plus ritonavir 100 mg twice daily for 2 weeks | 18 | ↑ 30; (↓ 15 to ↑ 47) | ↑ 37; (↓ 20 to ↑ 55) | ↑ 52; (↓ 28 to ↑ 82)
Maraviroc; 300 mg twice daily for 10 days | 700 mg twice daily plus ritonavir; 100 mg twice daily for; 20 days | 14 | ↑ 52; (↑ 27 to ↑ 82) | ↑ 149; (↑ 119 to ↑ 182) | ↑ 374; (↑ 303 to ↑ 457)
Maraviroc; 300 mg once daily for 10 days | 1,400 mg once daily; plus ritonavir; 100 mg once daily for; 20 days | 14 | ↑ 45; (↑ 20 to ↑ 74) | ↑ 126; (↑ 99 to ↑ 158) | ↑ 80; (↑ 53 to ↑ 113)
Methadone; 70 to 120 mg once daily for 2 weeks | 700 mg twice daily plus ritonavir 100 mg twice daily for 2 weeks | 19 | R-Methadone (active)
Methadone; 70 to 120 mg once daily for 2 weeks | 700 mg twice daily plus ritonavir 100 mg twice daily for 2 weeks | 19 | ↓ 21g; (↓ 30 to ↓ 12) | ↓ 18g; (↓ 27 to ↓ 8) | ↓ 11g; (↓ 21 to ↑ 1)
Methadone; 70 to 120 mg once daily for 2 weeks | 700 mg twice daily plus ritonavir 100 mg twice daily for 2 weeks | 19 | S-Methadone (inactive)
Methadone; 70 to 120 mg once daily for 2 weeks | 700 mg twice daily plus ritonavir 100 mg twice daily for 2 weeks | 19 | ↓ 43g; (↓ 49 to ↓ 37) | ↓ 43g; (↓ 50 to ↓ 36) | ↓ 41g; (↓ 49 to ↓ 31)
Nevirapine; 200 mg twice daily for; 2 weeksh | 1,400 mg twice daily for 2 weeks | 17 | ↑ 25; (↑ 14 to ↑ 37) | ↑ 29; (↑ 19 to ↑ 40) | ↑ 34; (↑ 20 to ↑ 49)
Nevirapine; 200 mg twice daily for 2 weeksh | 700 mg twice daily plus ritonavir 100 mg twice daily for 2 weeks | 17 | ↑ 13; (↑ 3 to ↑ 24) | ↑ 14; (↑ 5 to ↑ 24) | ↑ 22; (↑ 9 to ↑ 35)
Norethindronec; 0.5 mg once daily for 21 days | 700 mg twice daily plus ritonavir 100 mg twice daily for 21 days | 25 | ↓ 38; (↓ 32 to ↓ 44) | ↓ 34; (↓ 30 to ↓ 37) | ↓ 26; (↓ 20 to ↓ 32)
Phenytoin; 300 mg once daily for 10 days | 700 mg twice daily plus ritonavir 100 mg twice daily. for 10 days | 14 | ↓ 20; (↓ 12 to ↓ 27) | ↓ 22; (↓ 17 to ↓ 27) | ↓ 29; (↓ 23 to ↓ 34)
Rifabutin; 150 mg every other day for 2 weeksi | 700 mg twice daily plus ritonavir 100 mg twice daily for 2 weeks | 15 | ↓ 14; (↓ 28 to ↑ 4) | ↔ | ↑ 28; (↑ 12 to ↑ 46)
(25-O-desacetylrifabutin metabolite) | 700 mg twice daily plus ritonavir 100 mg twice daily for 2 weeks | 15 | ↑ 579; (↑ 479 to ↑ 698) | ↑ 1,120; (↑ 965 to ↑ 1,300) | ↑ 2,510; (↑ 1,910 to ↑ 3,300)
Rifabutin + 25-O-desacetylrifabutin metabolite | 700 mg twice daily plus ritonavir 100 mg twice daily for 2 weeks | 15 | NA | ↑ 64; (↑ 46 to ↑ 84) | NA
Rosuvastatin10 mg single dose | 700 mg twice dailyplus ritonavir100 mg twice dailyfor7 days |  | (↑ 45) | (↑ 8) | NA

aConcomitant medication is also shown in this column where appropriate.

bComparison arm of atazanavir 300 mg once daily plus ritonavir 100 mg once daily for 10 days.

cAdministered as a combination oral contraceptive tablet: ethinyl estradiol 0.035 mg/norethindrone 0.5 mg.

dSubjects were receiving fosamprenavir calcium/ritonavir for 10 days prior to the 4-day treatment period with both ketoconazole and fosamprenavir calcium/ritonavir.

eData represent lopinavir concentrations.

fCompared with lopinavir 400 mg/ritonavir 100 mg twice daily for 2 weeks.

gDose normalized to methadone 100 mg. The unbound concentration of the active moiety, R-methadone, was unchanged.

hSubjects were receiving nevirapine for at least 12 weeks prior to trial.

iComparison arm of rifabutin 300 mg once daily for 2 weeks. AUC is AUC(0-48 h).

↑ = Increase; ↓ = Decrease; ↔ = No change (↑ or ↓ less than 10%); ND = Interaction cannot be determined as Cminwas below the lower limit of quantitation.

Table 13. Drug Interactions: Pharmacokinetic Parameters for Coadministered Drug in the Presence of Amprenavir after Administration of Agenerase

Coadministered Drug(s) and Dose(s) | Dose of Agenerase | n | % Change in Pharmacokinetic Parameters of Coadministered Drug (90% CI)
Coadministered Drug(s) and Dose(s) | Dose of Agenerase | n | Cmax | AUC | Cmin
Abacavir; 300 mg twice daily for 2 to 3 weeks | 900 mg twice daily for 2 to 3 weeks | 4 | ↔a | ↔a | ↔a
Clarithromycin; 500 mg twice daily for 4 days | 1,200 mg twice daily for 4 days | 12 | ↓ 10; (↓ 24 to ↑ 7) | ↔ | ↔
Delavirdine; 600 mg twice daily for 10 days | 600 mg twice daily for 10 days | 9 | ↓ 47b | ↓ 61b | ↓ 88b
Ethinyl estradiol; 0.035 mg for 1 cycle | 1,200 mg twice daily for 28 days | 10 | ↔ | ↔ | ↑ 32; (↓ 3 to ↑ 79)
Indinavir; 800 mg 3 times a day for 2 weeks (fasted) | 750 mg or 800 mg 3 times a day for 2 weeks (fasted) | 9 | ↓ 22a | ↓ 38a | ↓ 27a
Ketoconazole; 400 mg single dose | 1,200 mg single dose | 12 | ↑ 19; (↑ 8 to ↑ 33) | ↑ 44; (↑ 31 to ↑ 59) | NA
Lamivudine; 150 mg single dose | 600 mg single dose | 11 | ↔ | ↔ | NA
Methadone; 44 to 100 mg once daily for> 30 days | 1,200 mg twice daily for 10 days | 16 | R-Methadone (active)
Methadone; 44 to 100 mg once daily for> 30 days | 1,200 mg twice daily for 10 days | 16 | ↓ 25; (↓ 32 to ↓ 18) | ↓ 13; (↓ 21 to ↓ 5) | ↓ 21; (↓ 32 to ↓ 9)
Methadone; 44 to 100 mg once daily for> 30 days | 1,200 mg twice daily for 10 days | 16 | S-Methadone (inactive)
Methadone; 44 to 100 mg once daily for> 30 days | 1,200 mg twice daily for 10 days | 16 | ↓ 48; (↓ 55 to ↓ 40) | ↓ 40; (↓ 46 to ↓ 32) | ↓ 53; (↓ 60 to ↓ 43)
Nelfinavir; 750 mg 3 times a day for 2 weeks (fed) | 750 mg or 800 mg 3 times a day for 2 weeks (fed) | 6 | ↑ 12a | ↑ 15a | ↑ 14a
Norethindrone; 1 mg for 1 cycle | 1,200 mg twice daily for 28 days | 10 | ↔ | ↑ 18; (↑ 1 to ↑ 38) | ↑ 45; (↑ 13 to ↑ 88)
Rifabutin; 300 mg once daily for 10 days | 1,200 mg twice daily for 10 days | 5 | ↑119; (↑ 82 to ↑ 164) | ↑193; (↑ 156 to ↑ 235) | ↑ 271; (↑ 171 to ↑ 409)
Rifampin; 300 mg once daily for 4 days | 1,200 mg twice daily for 4 days | 11 | ↔ | ↔ | ND
Saquinavir; 800 mg 3 times a day for 2 weeks (fed) | 750 mg or 800 mg 3 times a day for 2 weeks (fed) | 7 | ↑ 21a | ↓ 19a | ↓ 48a
Zidovudine; 300 mg single dose | 600 mg single dose | 12 | ↑ 40; (↑ 14 to ↑ 71) | ↑ 31; (↑ 19 to ↑ 45) | NA

aCompared with historical data.

bMedian percent change; confidence interval not reported.

↑ = Increase; ↓ = Decrease; ↔= No change (↑or ↓ less than 10%); NA = Cminnot calculated for single-dose trial; ND = Interaction cannot be determined as Cminwas below the lower limit of quantitation.

12.4 Microbiology

Mechanism of Action

Fosamprenavir is a prodrug that is rapidly hydrolyzed to amprenavir by cellular phosphatases in the gut epithelium as it is absorbed. Amprenavir is an inhibitor of HIV-1 protease. Amprenavir binds to the active site of HIV-1 protease and thereby prevents the processing of viral Gag and Gag-Pol polyprotein precursors, resulting in the formation of immature non-infectious viral particles.

Antiviral Activity

Fosamprenavir has little or no antiviral activity in cell culture. The antiviral activity of amprenavir was evaluated against HIV-1 IIIB in both acutely and chronically infected lymphoblastic cell lines (MT-4, CEM-CCRF, H9) and in peripheral blood lymphocytes in cell culture. The 50% effective concentration (EC50) of amprenavir ranged from 0.012 to 0.08 microM in acutely infected cells and was 0.41 microM in chronically infected cells (1 microM = 0.50 mcg per mL). The median EC50value of amprenavir against HIV-1 isolates from clades A to G was 0.00095 microM in peripheral blood mononuclear cells (PBMCs). Similarly, the EC50values for amprenavir against monocytes/macrophage tropic HIV-1 isolates (clade B) ranged from 0.003 to 0.075 microM in monocyte/macrophage cultures. The EC50values of amprenavir against HIV-2 isolates grown in PBMCs were higher than those for HIV-1 isolates, and ranged from 0.003 to 0.11 microM. The anti-HIV-1 activity of amprenavir was not antagonistic in combination with the nucleoside reverse transcriptase inhibitors (NRTIs); abacavir, didanosine, lamivudine, stavudine, tenofovir, and zidovudine; the non-nucleoside reverse transcriptase inhibitors (NNRTIs) delavirdine, efavirenz, and nevirapine; the protease inhibitors (PIs) atazanavir, indinavir, lopinavir, nelfinavir, ritonavir, and saquinavir; and the gp41 fusion inhibitor enfuvirtide. These drug combinations have not been adequately studied in humans.

Resistance

HIV-1 isolates with decreased susceptibility to amprenavir have been selected in cell culture and obtained from subjects treated with fosamprenavir. Genotypic analysis of isolates from treatment-naive subjects failing amprenavir-containing regimens showed substitutions in the HIV-1 protease resulting in amino acid substitutions primarily at positions V32I, M46I/L, I47V, I50V, I54L/M, and I84V, as well as substitutions in the p7/p1 and p1/p6 Gag and Gag-Pol polyprotein precursor cleavage sites. Some of these amprenavir resistance-associated substitutions have also been detected in HIV-1 isolates from antiretroviral-naive subjects treated with fosamprenavir calcium. Of the 488 antiretroviral-naive subjects treated with fosamprenavir calcium 1,400 mg twice daily or fosamprenavir calcium 1,400 mg plus ritonavir 200 mg once daily in Trials APV30001 and APV30002, respectively, isolates from 61 subjects (29 receiving fosamprenavir calcium and 32 receiving fosamprenavir calcium/ritonavir) with virologic failure (plasma HIV-1 RNA greater than 1,000 copies per mL on 2 occasions on or after Week 12) were genotyped. Isolates from 5 of the 29 antiretroviral-naive subjects (17%) receiving fosamprenavir calcium without ritonavir in Trial APV30001 had evidence of genotypic resistance to amprenavir: I54L/M (n = 2), I54L + L33F (n = 1), V32I + I47V (n = 1), and M46I + I47V (n = 1). No amprenavir resistance-associated substitutions were detected in isolates from antiretroviral-naive subjects treated with fosamprenavir calcium/ritonavir for 48 weeks in Trial APV30002. However, the M46I and I50V substitutions were detected in isolates from 1 virologic failure subject receiving fosamprenavir calcium/ritonavir once daily at Week 160 (HIV-1 RNA greater than 500 copies per mL). Upon retrospective analysis of stored samples using an ultrasensitive assay, these resistant substitutions were traced back to Week 84 (76 weeks prior to clinical virologic failure).

Cross-Resistance

Varying degrees of cross-resistance among HIV-1 protease inhibitors have been observed. An association between virologic response at 48 weeks (HIV-1 RNA level less than 400 copies per mL) and protease inhibitor-resistance substitutions detected in baseline HIV-1 isolates from protease inhibitor-experienced subjects receiving fosamprenavir calcium /ritonavir twice daily (n = 88), or lopinavir/ritonavir twice daily (n = 85) in Trial APV30003 is shown in Table 14. The majority of subjects had previously received either one (47%) or 2 protease inhibitors (36%), most commonly nelfinavir (57%) and indinavir (53%). Out of 102 subjects with baseline phenotypes receiving twice-daily fosamprenavir calcium/ritonavir, 54% (n = 55) had resistance to at least one protease inhibitor, with 98% (n = 54) of those having resistance to nelfinavir. Out of 97 subjects with baseline phenotypes in the lopinavir/ritonavir arm, 60% (n = 58) had resistance to at least one protease inhibitor, with 97% (n = 56) of those having resistance to nelfinavir.

Table 14. Responders at Trial Week 48 by Presence of Baseline Protease Inhibitor Resistance-Associated Substitutionsa

Protease Inhibitor Resistance‑ Associated Substitutionsb | Fosamprenavir Calcium/Ritonavir Twice Daily |  | Lopinavir/Ritonavir Twice Daily
Protease Inhibitor Resistance‑ Associated Substitutionsb | (n = 88) |  | (n = 85)
D30N | 21/22 | 95% | 17/19 | 89%
N88D/S | 20/22 | 91% | 12/12 | 100%
L90M | 16/31 | 52% | 17/29 | 59%
M46I/L | 11/22 | 50% | 12/24 | 50%
V82A/F/T/S | 2/9 | 22% | 6/17 | 35%
I54V | 2/11 | 18% | 6/11 | 55%
I84V | 1/6 | 17% | 2/5 | 40%

aResults should be interpreted with caution because the subgroups were small.

bMost subjects had greater than 1 protease inhibitor resistance-associated substitution at baseline.

The virologic response based upon baseline phenotype was assessed. Baseline isolates from protease inhibitor-experienced subjects responding to fosamprenavir calcium/ritonavir twice daily had a median shift in susceptibility to amprenavir relative to a standard wild-type reference strain of 0.7 (range: 0.1 to 5.4, n = 62), and baseline isolates from individuals failing therapy had a median shift in susceptibility of 1.9 (range: 0.2 to 14, n = 29). Because this was a select patient population, these data do not constitute definitive clinical susceptibility break points. Additional data are needed to determine clinically relevant break points for fosamprenavir calcium.

Isolates from 15 of the 20 subjects receiving twice-daily fosamprenavir calcium/ritonavir up to Week 48 and experiencing virologic failure/ongoing replication were subjected to genotypic analysis. The following amprenavir resistance-associated substitutions were found either alone or in combination: V32I, M46I/L, I47V, I50V, I54L/M, and I84V. Isolates from 4 of the 16 subjects continuing to receive twice-daily fosamprenavir calcium/ritonavir up to Week 96 who experienced virologic failure underwent genotypic analysis. Isolates from 2 subjects contained amprenavir resistance-associated substitutions: V32I, M46I, and I47V in 1 isolate and I84V in the other.

13 NONCLINICAL TOXICOLOGY

13.1 Carcinogenesis, Mutagenesis, Impairment of Fertility

In long-term carcinogenicity studies, fosamprenavir was administered orally for up to 104 weeks at doses of 250, 400, or 600 mg per kg per day in mice and at doses of 300, 825, or 2,250 mg per kg per day in rats. Exposures at these doses were 0.3- to 0.7-fold (mice) and 0.7- to 1.4-fold (rats) those in humans given 1,400 mg twice daily of fosamprenavir alone, and 0.2- to 0.3-fold (mice) and 0.3- to 0.7-fold (rats) those in humans given 1,400 mg once daily of fosamprenavir plus 200 mg ritonavir once daily. Exposures in the carcinogenicity studies were 0.1- to 0.3-fold (mice) and 0.3- to 0.6-fold (rats) those in humans given 700 mg of fosamprenavir plus 100 mg ritonavir twice daily. There was an increase in hepatocellular adenomas and hepatocellular carcinomas at all doses in male mice and at 600 mg per kg per day in female mice, and in hepatocellular adenomas and thyroid follicular cell adenomas at all doses in male rats, and at 825 mg per kg per day and 2,250 mg per kg per day in female rats. The relevance of the hepatocellular findings in the rodents for humans is uncertain. Repeat-dose studies with fosamprenavir in rats produced effects consistent with enzyme induction, which predisposes rats, but not humans, to thyroid neoplasms. In addition, in rats only there was an increase in interstitial cell hyperplasia at 825 mg per kg per day and 2,250 mg per kg per day, and an increase in uterine endometrial adenocarcinoma at 2,250 mg per kg per day. The incidence of endometrial findings was slightly increased over concurrent controls, but was within background range for female rats. The relevance of the uterine endometrial adenocarcinoma findings in rats for humans is uncertain.

Fosamprenavir was not mutagenic or genotoxic in a battery of in vitroand in vivoassays. These assays included bacterial reverse mutation (Ames), mouse lymphoma, rat micronucleus, and chromosome aberrations in human lymphocytes.

The effects of fosamprenavir on fertility and general reproductive performance were investigated in male (treated for 4 weeks before mating) and female rats (treated for 2 weeks before mating through Postpartum Day 6) that received doses of 300, 820, or 2,240 mg per kg per day. Systemic exposures (AUC0-24 h) to amprenavir in these studies were 3 (males) to 4 (females) times higher than exposures in humans following administration of the MRHD of fosamprenavir alone or similar to those seen in humans following administration of fosamprenavir in combination with ritonavir. Fosamprenavir did not impair mating or fertility of male or female rats and did not affect the development and maturation of sperm from treated rats.

14 CLINICAL STUDIES

14.1 Therapy-Naive Adult Trials

APV30001

A randomized, open-label trial evaluated treatment with fosamprenavir calcium tablets (1,400 mg twice daily) versus nelfinavir (1,250 mg twice daily) in 249 antiretroviral treatment-naive subjects. Both groups of subjects also received abacavir (300 mg twice daily) and lamivudine (150 mg twice daily).

The mean age of the subjects in this trial was 37 years (range: 17 to 70 years); 69% of the subjects were male, 20% were CDC Class C (AIDS), 24% were white, 32% were black, and 44% were Hispanic. At baseline, the median CD4+ cell count was 212 cells per mm^3(range: 2 to 1,136 cells per mm^3; 18% of subjects had a CD4+ cell count of less than 50 cells per mm^3and 30% were in the range of 50 to less than 200 cells per mm^3). Baseline median HIV-1 RNA was 4.83 log10copies per mL (range: 1.69 to 7.41 log10copies per mL; 45% of subjects had greater than 100,000 copies per mL).

The outcomes of randomized treatment are provided in Table 15.

Table 15. Outcomes of Randomized Treatment through Week 48 (APV30001)

Outcome; (Rebound or discontinuation = failure) | Fosamprenavir Calcium; 1,400 mg Twice Daily | Nelfinavir; 1,250 mg Twice Daily
Outcome; (Rebound or discontinuation = failure) | (n = 166) | (n = 83)
Respondera | 66% (57%) | 52% (42%)
Virologic failure | 19% | 32%
Rebound | 16% | 19%
Never suppressed through Week 48 | 3% | 13%
Clinical progression | 1% | 1%
Death | 0% | 1%
Discontinued due to adverse reactions | 4% | 2%
Discontinued due to other reasonsb | 10% | 10%

aSubjects achieved and maintained confirmed HIV-1 RNA less than 400 copies per mL (less than 50 copies per mL) through Week 48 (Roche AMPLICOR HIV-1 MONITOR Assay Version 1.5).

bIncludes consent withdrawn, lost to follow up, protocol violations, those with missing data, and other reasons.

Treatment response by viral load strata is shown in Table 16.

Table 16. Proportions of Responders through Week 48 by Screening Viral Load (APV30001)

Screening Viral Load HIV-1 RNA (copies/mL) | Fosamprenavir Calcium; 1,400 mg Twice Daily |  | Nelfinavir; 1,250 mg Twice Daily
Screening Viral Load HIV-1 RNA (copies/mL) | < 400 copies/mL | n | < 400 copies/mL | n
≤ 100,000 | 65% | 93 | 65% | 46
> 100,000 | 67% | 73 | 36% | 37

Through 48 weeks of therapy, the median increases from baseline in CD4+ cell counts were 201 cells per mm^3in the group receiving fosamprenavir calcium and 216 cells per mm^3in the nelfinavir group.

APV30002

A randomized, open-label trial evaluated treatment with fosamprenavir calcium tablets (1,400 mg once daily) plus ritonavir (200 mg once daily) versus nelfinavir (1,250 mg twice daily) in 649 treatment-naive subjects. Both treatment groups also received abacavir (300 mg twice daily) and lamivudine (150 mg twice daily).

The mean age of the subjects in this trial was 37 years (range: 18 to 69 years); 73% of the subjects were male, 22% were CDC Class C, 53% were white, 36% were black, and 8% were Hispanic. At baseline, the median CD4+ cell count was 170 cells per mm^3(range: 1 to 1,055 cells per mm^3; 20% of subjects had a CD4+ cell count of less than 50 cells per mm^3and 35% were in the range of 50 to less than 200 cells per mm^3). Baseline median HIV-1 RNA was 4.81 log10copies per mL (range: 2.65 to 7.29 log10copies per mL; 43% of subjects had greater than 100,000 copies per mL).

The outcomes of randomized treatment are provided in Table 17.

Table 17. Outcomes of Randomized Treatment through Week 48 (APV30002)

Outcome; (Rebound or discontinuation = failure) | Fosamprenavir Calcium; 1,400 mg/Ritonavir 200 mg Once Daily | Nelfinavir; 1,250 mg Twice Daily
Outcome; (Rebound or discontinuation = failure) | (n = 322) | (n = 327)
Respondera | 69% (58%) | 68% (55%)
Virologic failure | 6% | 16%
Rebound | 5% | 8%
Never suppressed through Week 48 | 1% | 8%
Death | 1% | 0%
Discontinued due to adverse reactions | 9% | 6%
Discontinued due to other reasonsb | 15% | 10%

aSubjects achieved and maintained confirmed HIV-1 RNA less than 400 copies per mL (less than 50 copies per mL) through Week 48 (Roche AMPLICOR HIV-1 MONITOR Assay Version 1.5).

bIncludes consent withdrawn, lost to follow up, protocol violations, those with missing data, and other reasons.

Treatment response by viral load strata is shown in Table 18.

Table 18. Proportions of Responders through Week 48 by Screening Viral Load (APV30002)

Screening Viral Load HIV-1 RNA (copies/mL) | Fosamprenavir Calcium; 1,400 mg/Ritonavir 200 mg Once Daily |  | Nelfinavir; 1,250 mg Twice Daily
Screening Viral Load HIV-1 RNA (copies/mL) | < 400 copies/mL | n | < 400 copies/mL | n
≤ 100,000 | 72% | 197 | 73% | 194
> 100,000 | 66% | 125 | 64% | 133

Through 48 weeks of therapy, the median increases from baseline in CD4+ cell counts were 203 cells per mm^3in the group receiving fosamprenavir calcium and 207 cells per mm^3in the nelfinavir group.

14.2 Protease Inhibitor-Experienced Adult Trials

APV30003

A randomized, open-label, multicenter trial evaluated 2 different regimens of fosamprenavir calcium plus ritonavir (fosamprenavir calcium tablets 700 mg twice daily plus ritonavir 100 mg twice daily or fosamprenavir calcium tablets 1,400 mg once daily plus ritonavir 200 mg once daily) versus lopinavir/ritonavir (400 mg/100 mg twice daily) in 315 subjects who had experienced virologic failure to 1 or 2 prior protease inhibitor-containing regimens.

The mean age of the subjects in this trial was 42 years (range: 24 to 72 years); 85% were male, 33% were CDC Class C, 67% were white, 24% were black, and 9% were Hispanic. The median CD4+ cell count at baseline was 263 cells per mm^3(range: 2 to 1,171 cells per mm^3). Baseline median plasma HIV-1 RNA level was 4.14 log10copies per mL (range: 1.69 to 6.41 log10copies per mL).

The median durations of prior exposure to NRTIs were 257 weeks for subjects receiving fosamprenavir calcium/ritonavir twice daily (79% had greater than or equal to 3 prior NRTIs) and 210 weeks for subjects receiving lopinavir/ritonavir (64% had greater than or equal to 3 prior NRTIs). The median durations of prior exposure to protease inhibitors were 149 weeks for subjects receiving fosamprenavir calcium/ritonavir twice daily (49% received greater than or equal to 2 prior protease inhibitors) and 130 weeks for subjects receiving lopinavir/ritonavir (40% received greater than or equal to 2 prior protease inhibitors).

The time-averaged changes in plasma HIV-1 RNA from baseline (AAUCMB) at 48 weeks (the endpoint on which the trial was powered) were -1.4 log10copies per mL for twice-daily fosamprenavir calcium/ritonavir and -1.67 log10copies per mL for the lopinavir/ritonavir group.

The proportions of subjects who achieved and maintained confirmed HIV-1 RNA less than 400 copies per mL (secondary efficacy endpoint) were 58% with twice-daily fosamprenavir calcium/ritonavir and 61% with lopinavir/ritonavir (95% CI for the difference: -16.6, 10.1). The proportions of subjects with HIV-1 RNA less than 50 copies per mL with twice-daily fosamprenavir calcium/ritonavir and with lopinavir/ritonavir were 46% and 50%, respectively (95% CI for the difference: -18.3, 8.9). The proportions of subjects who were virologic failures were 29% with twice-daily fosamprenavir calcium/ritonavir and 27% with lopinavir/ritonavir.

The frequency of discontinuations due to adverse events and other reasons, and deaths were similar between treatment arms.

Through 48 weeks of therapy, the median increases from baseline in CD4+ cell counts were 81 cells per mm^3with twice-daily fosamprenavir calcium/ritonavir and 91 cells per mm^3with lopinavir/ritonavir.

This trial was not large enough to reach a definitive conclusion that fosamprenavir calcium/ritonavir and lopinavir/ritonavir are clinically equivalent.

Once-daily administration of fosamprenavir calcium plus ritonavir is not recommended for protease inhibitor-experienced patients. Through Week 48, 50% and 37% of subjects receiving fosamprenavir calcium 1,400 mg plus ritonavir 200 mg once daily had plasma HIV-1 RNA less than 400 copies per mL and less than 50 copies per mL, respectively.

14.3 Pediatric Trials

Three open-label trials in pediatric subjects aged at least 4 weeks to 18 years were conducted. In one trial (APV29005), twice-daily dosing regimens (fosamprenavir calcium with or without ritonavir) were evaluated in combination with other antiretroviral agents in pediatric subjects aged 2 to 18 years. In a second trial (APV20002), twice-daily dosing regimens (fosamprenavir calcium with ritonavir) were evaluated in combination with other antiretroviral agents in pediatric subjects aged at least 4 weeks to younger than 2 years. A third trial (APV20003) evaluated once-daily dosing of fosamprenavir calcium with ritonavir; the pharmacokinetic data from this trial did not support a once-daily dosing regimen in any pediatric patient population.

APV29005

Fosamprenavir calcium:Twenty (18 therapy-naive and 2 therapy-experienced) pediatric subjects received fosamprenavir calcium oral suspension without ritonavir twice daily. At Week 24, 65% (13 of 20) achieved HIV-1 RNA less than 400 copies per mL, and the median increase from baseline in CD4+ cell count was 350 cells per mm^3.

Fosamprenavir calcium plus Ritonavir:Forty-nine protease inhibitor-naive and 40 protease inhibitor-experienced pediatric subjects received fosamprenavir calcium oral suspension or tablets with ritonavir twice daily. At Week 24, 71% of protease inhibitor-naive (35 of 49) and 55% of protease inhibitor-experienced (22 of 40) subjects achieved HIV-1 RNA less than 400 copies per mL; median increases from baseline in CD4+ cell counts were 184 cells per mm^3and 150 cells per mm^3in protease inhibitor-naive and experienced subjects, respectively.

APV20002

Fifty-four pediatric subjects (49 protease inhibitor-naive and 5 protease inhibitor-experienced) received fosamprenavir calcium oral suspension with ritonavir twice daily. At Week 24, 72% of subjects achieved HIV-1 RNA less than 400 copies per mL. The median increases from baseline in CD4+ cell counts were 400 cells per mm^3in subjects aged at least 4 weeks to younger than 6 months and 278 cells per mm^3in subjects aged 6 months to 2 years.

16 HOW SUPPLIED/STORAGE AND HANDLING

Fosamprenavir calcium tablets, USP, 700 mg, are pink colored, coated, oval-shaped tablets with “RJ47”imprinted on one side with black ink and plain on the other side. They are supplied as follows-

NDC 63304-583-30 Bottles of 30 with child-resistant closure

NDC 63304-583-60 Bottles of 60 with child-resistant closure

NDC 63304-583-01 Bottles of 100

Store at 20° C to 25° C (68° F to 77° F) [See USP Controlled Room Temperature].

Keep bottle tightly closed. Protect from moisture.

17 PATIENT COUNSELING INFORMATION

Advise the patient to read the FDA-approved patient labeling (Patient Information).

Drug Interactions

A statement to patients and healthcare providers is included on the product’s bottle label: ALERT: Find out about medicines that should NOT be taken with fosamprenavir calcium tablets.

Fosamprenavir calcium tablets may interact with many drugs; therefore, advise patients to report to their healthcare provider the use of any other prescription or nonprescription medication or herbal products, particularly St. John’s wort.

Advise patients receiving PDE5 inhibitors that they may be at an increased risk of PDE5 inhibitor-associated adverse events, including hypotension, visual changes, and priapism, and should promptly report any symptoms to their healthcare provider [see Contraindications (4), Warnings and Precautions (5.1), Drug Interactions (7)].

Contraception

Instruct patients receiving combined hormonal contraception to use an effective alternative contraceptive method or an additional barrier method during therapy with fosamprenavir calcium tablets because hormonal levels may decrease, and if used in combination with fosamprenavir calcium tablets and ritonavir, liver enzyme elevations may occur [see Drug Interactions (7.2), Use in Specific Populations (8.3)].

Severe Skin Reactions

Advise patients that skin reactions ranging from mild to severe, including Stevens-Johnson Syndrome, have been reported with fosamprenavir calcium tablets. Advise patients to discontinue fosamprenavir calcium tablets immediately for severe or life-threatening skin reactions or for moderate rashes accompanied by systemic symptoms [see Warnings and Precautions (5.2), Adverse Reactions (6)].

Sulfa Allergy

Advise patients to inform their healthcare provider if they have a sulfa allergy. The potential for cross-sensitivity between drugs in the sulfonamide class and fosamprenavir is unknown [see Warnings and Precautions (5.3)].

Hepatic Toxicity

Advise patients that it is recommended to have laboratory testing before and during therapy as patients with underlying hepatitis B or C or marked elevations of transaminases prior to treatment may be at increased risk for developing or worsening transaminase elevations with use of fosamprenavir calcium tablets, particularly at higher than recommended doses which should not be used. [see Warnings and Precautions (5.4)].

Immune Reconstitution Syndrome

Advise patients to inform their healthcare provider immediately of any signs or symptoms of infection as inflammation from previous infection may occur soon after combination antiretroviral therapy, including when fosamprenavir calcium tablets is started [see Warnings and Precautions (5.6)].

Increase in Body Fat

Inform patients that an increase of body fat may occur in patients receiving protease inhibitors, including fosamprenavir calcium tablets, and that the cause and long-term health effects of these conditions are not known at this time [see Warnings and Precautions (5.7)].

Lipid Elevations

Advise patients that it is recommended to have laboratory testing before and during therapy as increases in the concentration of triglycerides and cholesterol have been reported with use of fosamprenavir calcium tablets [see Warnings and Precautions (5.8), Adverse Reactions (6)].

Pregnancy Registry

Advise patients that there is a pregnancy exposure registry that monitors pregnancy outcomes in women exposed to fosamprenavir calcium tablets during pregnancy [see Use in Specific Populations (8.1)].

Lactation

Instruct women with HIV-1 infection not to breastfeed because HIV-1 can be passed to the baby in the breast milk [see Use in Specific Populations (8.2)].

Missed Dose

Instruct patients that if they miss a dose of fosamprenavir calcium tablets, to take it as soon as they remember. Advise patients not to double their next dose or take more than the prescribed dose [see Dosage and Administration (2)].

All trademarks are the property of their respective owners.

Manufactured by:

Ohm Laboratories Inc.

New Brunswick, NJ 08901

Distributed by:

Sun Pharmaceutical Industries, Inc.

Cranbury, NJ 08512

June 2024 FDA-06

Patient Information available at https://www.sunpharma.com/usa/products

PATIENT INFORMATION

Patient Information available at https://www.sunpharma.com/usa/products

FOSAMPRENAVIR (foss-am-PREN-ah-ver) CALCIUM TABLETS, USP

Rx only

What is the most important information I should know about fosamprenavir calcium tablets?

Fosamprenavir calcium tablets can interact with other medicines and cause serious side effects. It is important to know the medicines that should not be taken with fosamprenavir calcium tablets. See the section “Who should not take fosamprenavir calcium tablets?”

Fosamprenavir calcium tablets can cause serious side effects, including:

- Severe skin reactions.fosamprenavir calcium tablets may cause severe or life-threatening skin reactions or rash.

If you get a rash with any of the following symptoms, stop taking fosamprenavir calcium tablets and call your healthcare provider or get medical help right away:

- hives or sores in your mouth, or your skin blisters and peels
- swelling of your face, eyes, lips, tongue, or throat
- trouble swallowing or breathing

For more information about side effects, see “What are the possible side effects of fosamprenavir calcium tablets?”

What are fosamprenavir calcium tablets?

Fosamprenavir calcium tablets are prescription medicines that are used together with other antiretroviral medicines to treat human immunodeficiency virus 1 (HIV-1) infection.

HIV-1 is the virus that causes Acquired Immune Deficiency Syndrome (AIDS).

It is not known if fosamprenavir calcium tablets are safe and effective in children younger than 4 weeks of age.

Do not take fosamprenavir calcium tablets if you:

- are allergicto amprenavir, fosamprenavir calcium, or any of the ingredients in fosamprenavir calcium tablets. See the end of this leaflet for a complete list of ingredients in fosamprenavir calcium tablets.
- take any of the following medicines:
- alfuzosin
- rifampin
- ergot including:
- dihydroergotamine mesylate
- ergonovine
- ergotamine tartrate
- methylergonovine
- cisapride
- St. John’s wort (Hypericum perforatum)
- lomitapide
- lovastatin
- simvastatin
- pimozide
- delavirdine mesylate
- sildenafil (Revatio), for treatment of pulmonary arterial hypertension
- triazolam
- midazolam, when taken by mouth

Serious problems can happen if you or your child take any of the medicines listed above with fosamprenavir calcium tablets.

If you are taking fosamprenavir calcium tablets with ritonavir, do not take the following medicines:

- flecainide
- propafenone
- lurasidone

Before taking fosamprenavir calcium tablets, tell your healthcare provider about all of your medical conditions, including if you:

- are allergic to medicines that contain sulfa.
- have or have had liver problems, including hepatitis B or C virus infection.
- have kidney problems.
- have high blood sugar (diabetes).
- have hemophilia.
- have high cholesterol.
- are pregnant or plan to become pregnant. It is not known if fosamprenavir calcium tablets will harm your unborn baby. Talk to your healthcare provider if you are pregnant or plan to become pregnant during treatment with fosamprenavir calcium tablets.
  - fosamprenavir calcium tablets may reduce how well hormonal contraceptives (birth control pills) work. Females who may become pregnant should use a different form of birth control or an additional barrier method of birth control during treatment with fosamprenavir calcium tablets.

Pregnancy Registry.There is a pregnancy registry for women who take fosamprenavir calcium tablets during pregnancy. The purpose of the registry is to collect information about the health of you and your baby. Talk to your healthcare provider about how you can take part in this registry.

- are breastfeeding or plan to breastfeed. Do not breastfeed if you take fosamprenavir calcium tablets.
  - You should not breastfeed if you have HIV-1 because of the risk of passing HIV-1 to your baby.
  - It is not known if fosamprenavir calcium tablets can pass to your baby in your breast milk.
  - Talk with your healthcare provider about the best way to feed your baby.

Tell your healthcare provider about all the medicines you take,including prescription and over-the-counter medicines, vitamins, and herbal supplements. Some medicines interact with fosamprenavir calcium tablets. Keep a list of your medicines to show your healthcare provider and pharmacist.

- You can ask your healthcare provider or pharmacist for a list of medicines that interact with fosamprenavir calcium tablets.
- Do not start taking a new medicine without telling your healthcare provider.Your healthcare provider can tell you if it is safe to take fosamprenavir calcium tablets with other medicines.

How should I take fosamprenavir calcium tablets?

- Take fosamprenavir calcium tablets exactly as your healthcare provider tells you to take it.
- If you miss a dose of fosamprenavir calcium tablets, take it as soon as you remember. Do not take 2 doses at the same time or take more than your healthcare provider tells you to take.
- Stay under the care of a healthcare provider during treatment with fosamprenavir calcium tablets.
- If your child is taking fosamprenavir calcium tablets, your child’s healthcare provider will decide the right dose based on your child’s weight.
- fosamprenavir calcium tablets tablets may be taken with or without food.
- Do not run out of fosamprenavir calcium tablets. The virus in your blood may increase and the virus may become harder to treat. When your supply starts to run low, get more from your healthcare provider or pharmacy.
- If you take too much fosamprenavir calcium tablets, call your healthcare provider or go to the nearest hospital emergency room right away.

What are the possible side effects of fosamprenavir calcium tablets?

Fosamprenavir calcium tablets may cause serious side effects including:

- See “What is the most important information I should know about fosamprenavir calcium tablets?”
- Liver problems.Your healthcare provider should do blood tests before and during your treatment with fosamprenavir calcium tablets to check your liver function. Some people with liver problems, including hepatitis B or C, may have an increased risk of developing worsening liver problems during treatment with fosamprenavir calcium tablets.
- Diabetes and high blood sugar (hyperglycemia).Some people who take protease inhibitors, including fosamprenavir calcium tablets, can get high blood sugar, develop diabetes, or your diabetes can get worse. Tell your healthcare provider if you notice an increase in thirst or urinate often during treatment with fosamprenavir calcium tablets.
- Changes in your immune system (Immune Reconstitution Syndrome)can happen when you start taking HIV-1 medicines. Your immune system may get stronger and begin to fight infections that have been hidden in your body for a long time. Call your healthcare provider right away if you start having new symptoms after starting your HIV-1 medicine.
- Increase in body fat.An increase in body fat can happen in people who take protease inhibitors, including fosamprenavir calcium tablets. The exact cause and long-term health effects of these conditions are not known.
- Changes in blood tests.Some people have changes in blood tests while taking fosamprenavir calcium tablets. These include an increase in liver function tests, blood fat levels (cholesterol and triglycerides) and decrease in red blood cells. Your healthcare provider should do regular blood tests before and during your treatment with fosamprenavir calcium tablets.
- Increased bleeding problems in some people with hemophilia.Some people with hemophilia have increased bleeding with protease inhibitors, including fosamprenavir calcium tablets.
- Kidney stones.Some people have developed kidney stones during treatment with fosamprenavir calcium tablets. Tell your healthcare provider right away if you develop any of the following signs or symptoms of kidney stones:
  - pain in your side
  - blood in your urine
  - pain when you urinate

The most common side effects of fosamprenavir calcium tablets in adults include:

- nausea
- diarrhea
- vomiting
- headache
- rash

The most common side effects of fosamprenavir calcium tablets in children includevomiting and decrease in white blood cells. These are not all the possible side effects of fosamprenavir calcium tablets.

Call your doctor for medical advice about side effects. You may report side effects to FDA at 1-800-FDA-1088.

How should I store fosamprenavir calcium tablets?

- Store fosamprenavir calcium tablets at room temperature between 68° F to 77° F (20° C to 25° C).
- Keep the bottle of fosamprenavir calcium tablets tightly closed. Protect from moisture.

Keep fosamprenavir calcium tablets and all medicines out of the reach of children.

General information about the safe and effective use of fosamprenavir calcium tablets.

Medicines are sometimes prescribed for purposes other than those listed in a Patient Information leaflet. Do not use fosamprenavir calcium tablets for a condition for which it was not prescribed. Do not give fosamprenavir calcium tablets to other people, even if they have the same symptoms you have. It may harm them. You can ask your pharmacist or healthcare provider for information about fosamprenavir calcium tablets that is written for health professionals.

What are the ingredients in fosamprenavir calcium tablets?

Active ingredient:fosamprenavir calcium

Inactive ingredients:colloidal silicon dioxide, croscarmellose sodium, magnesium stearate, microcrystalline cellulose, and povidone. The tablet coating contains the inactive ingredients ethylcellulose, ferric oxide red, hypromellose, talc, and titanium dioxide. The imprinting ink contains the inactive ingredients ferric oxide black, propylene glycol, and shellac.

This Patient Information has been approved by the U.S. Food and Drug Administration.

All trademarks are the property of their respective owners.

Manufactured by:

Ohm Laboratories Inc.

New Brunswick, NJ 08901

Distributed by:

Sun Pharmaceutical Industries, Inc.

Cranbury, NJ 08512

June 2024 FDA-06

PACKAGE/LABEL PRINCIPAL DISPLAY PANEL

NDC 63304-583-60

Fosamprenavir Calcium Tablets

700 mg*

ALERT: Find out about medicines that should NOT be taken with Fosamprenavir Calcium Tablets.

Note to Pharmacist: Do not cover ALERT box with pharmacy label.

Rx only

60 Tablets ohm®